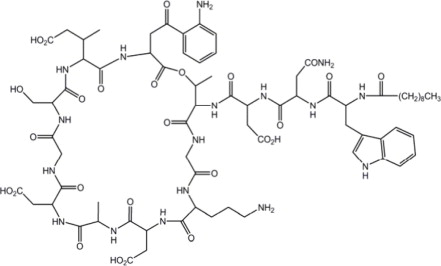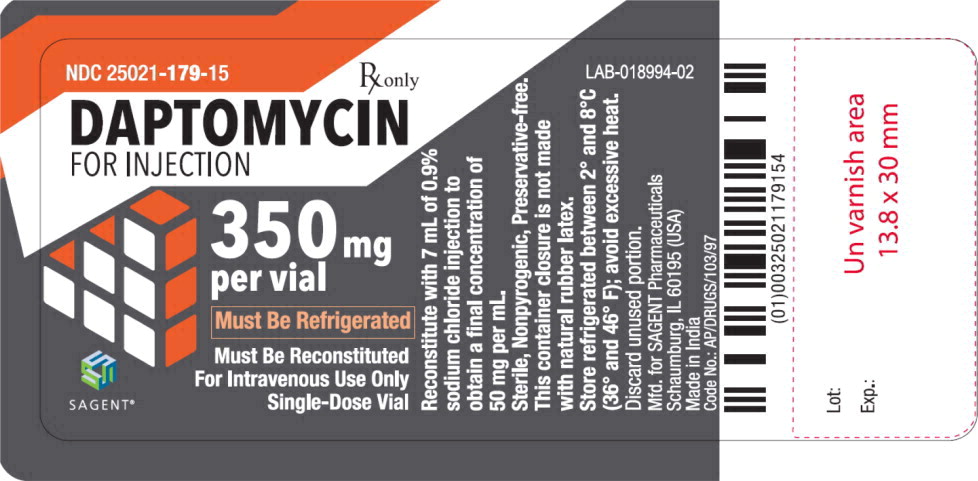 DRUG LABEL: Daptomycin
NDC: 25021-179 | Form: INJECTION, POWDER, LYOPHILIZED, FOR SOLUTION
Manufacturer: Sagent Pharmaceuticals
Category: prescription | Type: HUMAN PRESCRIPTION DRUG LABEL
Date: 20231001

ACTIVE INGREDIENTS: Daptomycin 350 mg/7 mL
INACTIVE INGREDIENTS: sodium hydroxide

HIGHLIGHTS OF PRESCRIBING INFORMATION

These highlights do not include all the information needed to use DAPTOMYCIN FOR INJECTION safely and effectively. See full prescribing information for DAPTOMYCIN FOR INJECTION.
DAPTOMYCIN for injection, for intravenous use
Initial U.S. Approval: 2003

RECENT MAJOR CHANGES

Warnings and Precautions, Development of Drug-Resistant Bacteria (5.12) | 10/2021

1 INDICATIONS AND USAGE

Daptomycin for Injection is a lipopeptide antibacterial indicated for the treatment of:

- Complicated skin and skin structure infections (cSSSI) in adult and pediatric patients (1 to 17 years of age) (1.1) and,
- Staphylococcus aureus bloodstream infections (bacteremia), in adult patients including those with right-sided infective endocarditis, (1.2)
- Staphylococcus aureus bloodstream infections (bacteremia) in pediatric patients (1 to 17 years of age). (1.3)

Limitations of Use:

- Daptomycin for Injection is not indicated for the treatment of pneumonia. (1.4)
- Daptomycin for Injection is not indicated for the treatment of left-sided infective endocarditis due to S. aureus. (1.4)
- Daptomycin for Injection is not recommended in pediatric patients younger than one year of age due to the risk of potential effects on muscular, neuromuscular, and/or nervous systems (either peripheral and/or central) observed in neonatal dogs. (1.4)

To reduce the development of drug-resistant bacteria and maintain the effectiveness of Daptomycin for Injection and other antibacterial drugs, Daptomycin for Injection should be used to treat or prevent infections that are proven or strongly suspected to be caused by bacteria. (1.5)

2 DOSAGE AND ADMINISTRATION

Adult Patients

- Administer to adult patients intravenously in 0.9% sodium chloride, either by injection over a 2-minute period or by infusion over a 30-minute period. (2.1, 2.7)
- Recommended dosage regimen for adult patients (2.2, 2.4, 2.6):

Creatinine Clearance (CLCR) | Dosage Regimen
Creatinine Clearance (CLCR) | cSSSI For 7 to 14 days | S. aureus Bacteremia For 2 to 6 weeks
≥30 mL/min | 4 mg/kg once every 24 hours | 6 mg/kg once every 24 hours
<30 mL/min, including hemodialysis and CAPD | 4 mg/kg once every 48 hours* | 6 mg/kg once every 48 hours*
*Administered following hemodialysis on hemodialysis days.

Pediatric Patients

- Unlike in adults, do NOT administer by injection over a two (2) minute period to pediatric patients. (2.1, 2.7)
- Administer to pediatric patients intravenously in 0.9% sodium chloride, by infusion over a 30- or 60-minute period, based on age. (2.1, 2.7)
- Recommended dosage regimen for pediatric patients (1 to 17 years of age) with cSSSI, based on age (2.3):

Age group | Dosage* | Duration of therapy
12 to 17 years | 5 mg/kg once every 24 hours infused over 30 minutes | Up to 14 days
7 to 11 years | 7 mg/kg once every 24 hours infused over 30 minutes | Up to 14 days
2 to 6 years | 9 mg/kg once every 24 hours infused over 60 minutes | Up to 14 days
1 to less than 2 years | 10 mg/kg once every 24 hours infused over 60 minutes | Up to 14 days
*Recommended dosage is for pediatric patients (1 to 17 years of age) with normal renal function. Dosage adjustment for pediatric patients with renal impairment has not been established.

- Recommended dosage regimen for pediatric patients (1 to 17 years of age) with S. aureus bacteremia, based on age (2.5):

Age group | Dosage* | Duration of therapy
12 to 17 years | 7 mg/kg once every 24 hours infused over 30 minutes | Up to 42 days
7 to 11 years | 9 mg/kg once every 24 hours infused over 30 minutes | Up to 42 days
1 to 6 years | 12 mg/kg once every 24 hours infused over 60 minutes | Up to 42 days
*Recommended dosage is for pediatric patients (1 to 17 years of age) with normal renal function. Dosage adjustment for pediatric patients with renal impairment has not been established.

- There are other formulations of daptomycin that have differences concerning storage and reconstitution. Carefully follow the reconstitution and storage procedures in labeling. (2.7)
- Do not use in conjunction with ReadyMED® elastomeric infusion pumps in adult and pediatric patients. (2.9)

3 DOSAGE FORMS AND STRENGTHS

For Injection: 350 mg lyophilized powder for reconstitution in a single-dose vial (3)

4 CONTRAINDICATIONS

- Known hypersensitivity to daptomycin (4)

5 WARNINGS AND PRECAUTIONS

- Anaphylaxis/hypersensitivity reactions (including life-threatening): Discontinue daptomycin and treat signs/symptoms. (5.1)
- Myopathy and rhabdomyolysis: Monitor CPK levels and follow muscle pain or weakness; if elevated CPK or myopathy occurs, consider discontinuation of daptomycin. (5.2)
- Eosinophilic pneumonia: Discontinue daptomycin and consider treatment with systemic steroids. (5.3)
- Drug Reaction with Eosinophilia and Systemic Symptoms (DRESS): Discontinue daptomycin and institute appropriate treatment. (5.4)
- Tubulointerstitial Nephritis (TIN): Discontinue daptomycin and institute appropriate treatment. (5.5)
- Peripheral neuropathy: Monitor for neuropathy and consider discontinuation. (5.6)
- Potential nervous system and/or muscular system effects in pediatric patients younger than 12 months: Avoid use of daptomycin in this age group. (5.7)
- Clostridioides difficile–associated diarrhea: Evaluate patients if diarrhea occurs. (5.8)
- Persisting or relapsing S. aureus bacteremia/endocarditis: Perform susceptibility testing and rule out sequestered foci of infection. (5.9)
- Decreased efficacy was observed in adult patients with moderate baseline renal impairment. (5.10)

6 ADVERSE REACTIONS

- Adult cSSSI Patients: The most common adverse reactions that occurred in ≥2% of adult cSSSI patients receiving daptomycin 4 mg/kg were diarrhea, headache, dizziness, rash, abnormal liver function tests, elevated creatine phosphokinase (CPK), urinary tract infections, hypotension, and dyspnea. (6.1)
- Pediatric cSSSI Patients: The most common adverse reactions that occurred in ≥2% of pediatric patients receiving daptomycin were diarrhea, vomiting, abdominal pain, pruritus, pyrexia, elevated CPK, and headache. (6.1)
- Adult S. aureus bacteremia/endocarditis Patients: The most common adverse reactions that occurred in ≥5% of S. aureus bacteremia/endocarditis patients receiving daptomycin 6 mg/kg were sepsis, bacteremia, abdominal pain, chest pain, edema, pharyngolaryngeal pain, pruritus, increased sweating, insomnia, elevated CPK, and hypertension. (6.1)
- Pediatric S. aureus bacteremia Patients: The most common adverse reactions that occurred in ≥5% of pediatric patients receiving daptomycin were vomiting and elevated CPK. (6.1)

To report SUSPECTED ADVERSE REACTIONS, contact Sagent Pharmaceuticals at 1-866-625-1618 or FDA at 1-800-FDA-1088 or www.fda.gov/medwatch.

FULL PRESCRIBING INFORMATION

1 INDICATIONS AND USAGE

1.1 Complicated Skin and Skin Structure Infections (cSSSI)

Daptomycin for Injection is indicated for the treatment of adult and pediatric patients (1 to 17 years of age) with complicated skin and skin structure infections (cSSSI) caused by susceptible isolates of the following Gram-positive bacteria: Staphylococcus aureus (including methicillin-resistant isolates), Streptococcus pyogenes, Streptococcus agalactiae, Streptococcus dysgalactiae subsp. equisimilis, and Enterococcus faecalis (vancomycin-susceptible isolates only).

1.2 Staphylococcus aureus Bloodstream Infections (Bacteremia) in Adult Patients, Including Those with Right-Sided Infective Endocarditis, Caused by Methicillin-Susceptible and Methicillin-Resistant Isolates

Daptomycin for Injection is indicated for the treatment of adult patients with Staphylococcus aureus bloodstream infections (bacteremia), including adult patients with right-sided infective endocarditis, caused by methicillin-susceptible and methicillin-resistant isolates.

1.3 Staphylococcus aureus Bloodstream Infections (Bacteremia) in Pediatric Patients (1 to 17 Years of Age)

Daptomycin for Injection is indicated for the treatment of pediatric patients (1 to 17 years of age) with Staphylococcus aureus bloodstream infections (bacteremia).

1.4 Limitations of Use

Daptomycin for Injection is not indicated for the treatment of pneumonia.

Daptomycin for Injection is not indicated for the treatment of left-sided infective endocarditis due to S. aureus. The clinical trial of Daptomycin for Injection in adult patients with S. aureus bloodstream infections included limited data from patients with left-sided infective endocarditis; outcomes in these patients were poor [see Clinical Studies (14.2)]. Daptomycin for Injection has not been studied in patients with prosthetic valve endocarditis.

Daptomycin for Injection is not recommended in pediatric patients younger than 1 year of age due to the risk of potential effects on muscular, neuromuscular, and/or nervous systems (either peripheral and/or central) observed in neonatal dogs [see Warnings and Precautions (5.7) and Nonclinical Toxicology (13.2)].

1.5 Usage

Appropriate specimens for microbiological examination should be obtained in order to isolate and identify the causative pathogens and to determine their susceptibility to daptomycin.

To reduce the development of drug-resistant bacteria and maintain the effectiveness of Daptomycin for Injection and other antibacterial drugs, Daptomycin for Injection should be used only to treat or prevent infections that are proven or strongly suspected to be caused by susceptible bacteria.

When culture and susceptibility information is available, it should be considered in selecting or modifying antibacterial therapy. In the absence of such data, local epidemiology and susceptibility patterns may contribute to the empiric selection of therapy. Empiric therapy may be initiated while awaiting test results.

2 DOSAGE AND ADMINISTRATION

2.1 Important Administration Duration Instructions

Adults

Administer the appropriate volume of the reconstituted Daptomycin for Injection (concentration of 50 mg per mL) to adult patients intravenously either by injection over a two (2) minute period or by intravenous infusion over a thirty (30) minute period [see Dosage and Administration (2.2, 2.4, 2.7)].

Pediatric Patients (1 to 17 Years of Age)

Unlike in adults, do NOT administer Daptomycin for Injection by injection over a two (2) minute period to pediatric patients.

- Pediatric Patients 7 to 17 years of Age: Administer Daptomycin for Injection intravenously by infusion over a 30-minute period [see Dosage and Administration (2.3, 2.5, 2.7)].
- Pediatric Patients 1 to 6 years of Age: Administer Daptomycin for Injection intravenously by infusion over a 60-minute period [see Dosage and Administration (2.3, 2.5, 2.7)].

2.2 Dosage in Adults for cSSSI

Administer Daptomycin for Injection 4 mg/kg to adult patients intravenously in 0.9% sodium chloride injection once every 24 hours for 7 to 14 days.

2.3 Dosage in Pediatric Patients (1 to 17 Years of Age) for cSSSI

The recommended dosage regimens based on age for pediatric patients with cSSSI are shown in Table 1. Administer Daptomycin for Injection intravenously in 0.9% sodium chloride injection once every 24 hours for up to 14 days.

Table 1: Recommended Dosage of Daptomycin for Injection in Pediatric Patients (1 to 17 Years of Age) with cSSSI, Based on Age
Age Range | Dosage Regimen* | Duration of therapy
12 to 17 years | 5 mg/kg once every 24 hours infused over 30 minutes | Up to 14 days
7 to 11 years | 7 mg/kg once every 24 hours infused over 30 minutes | Up to 14 days
2 to 6 years | 9 mg/kg once every 24 hours infused over 60 minutes | Up to 14 days
1 to less than 2 years | 10 mg/kg once every 24 hours infused over 60 minutes | Up to 14 days
*Recommended dosage regimen is for pediatric patients (1 to 17 years of age) with normal renal function. Dosage adjustment for pediatric patients with renal impairment has not been established.

2.4 Dosage in Adult Patients with Staphylococcus aureus Bloodstream Infections (Bacteremia), Including Those with Right-Sided Infective Endocarditis, Caused by Methicillin-Susceptible and Methicillin-Resistant Isolates

Administer Daptomycin for Injection 6 mg/kg to adult patients intravenously in 0.9% sodium chloride injection once every 24 hours for 2 to 6 weeks. There are limited safety data for the use of Daptomycin for Injection for more than 28 days of therapy. In the Phase 3 trial, there were a total of 14 adult patients who were treated with daptomycin for more than 28 days.

2.5 Dosage in Pediatric Patients (1 to 17 Years of Age) with Staphylococcus aureus Bloodstream Infections (Bacteremia)

The recommended dosage regimens based on age for pediatric patients with S. aureus bloodstream infections (bacteremia) are shown in Table 2. Administer Daptomycin for Injection intravenously in 0.9% sodium chloride injection once every 24 hours for up to 42 days.

Table 2: Recommended Dosage of Daptomycin for Injection in Pediatric Patients (1 to 17 Years of Age) with S. aureus Bacteremia, Based on Age
Age group | Dosage* | Duration of therapy
12 to 17 years | 7 mg/kg once every 24 hours infused over 30 minutes | Up to 42 days
7 to 11 years | 9 mg/kg once every 24 hours infused over 30 minutes | Up to 42 days
1 to 6 years | 12 mg/kg once every 24 hours infused over 60 minutes | Up to 42 days
*Recommended dosage is for pediatric patients (1 to 17 years of age) with normal renal function. Dosage adjustment for pediatric patients with renal impairment has not been established.

2.6 Dosage in Patients with Renal Impairment

Adult Patients

No dosage adjustment is required in adult patients with creatinine clearance (CLCR) greater than or equal to 30 mL/min. The recommended dosage regimen for Daptomycin for Injection in adult patients with CLCR less than 30 mL/min, including adult patients on hemodialysis or continuous ambulatory peritoneal dialysis (CAPD), is 4 mg/kg (cSSSI) or 6 mg/kg (S. aureus bloodstream infections) once every 48 hours (Table 3). When possible, Daptomycin for Injection should be administered following the completion of hemodialysis on hemodialysis days [see Warnings and Precautions (5.2, 5.10), Use in Specific Populations (8.6), and Clinical Pharmacology (12.3)].

Table 3: Recommended Dosage of Daptomycin for Injection in Adult Patients
Creatinine Clearance (CLCR) | Dosage Regimen in Adults
Creatinine Clearance (CLCR) | cSSSI | S. aureus Bloodstream Infections
Greater than or equal to 30 mL/min | 4 mg/kg once every 24 hours | 6 mg/kg once every 24 hours
Less than 30 mL/min, including hemodialysis and CAPD | 4 mg/kg once every 48 hours* | 6 mg/kg once every 48 hours*
*When possible, administer Daptomycin for Injection following the completion of hemodialysis on hemodialysis days.

Pediatric Patients

The dosage regimen for Daptomycin for Injection in pediatric patients with renal impairment has not been established.

2.7 Preparation and Administration of Daptomycin for Injection

There are other formulations of daptomycin that have differences concerning reconstitution and storage. Carefully follow the reconstitution and storage procedures described in this labeling.

Reconstitution of Daptomycin for Injection Vial

Daptomycin for Injection is supplied in single-dose vials, each containing 350 mg daptomycin as a sterile, lyophilized powder. The contents of a Daptomycin for Injection vial should be reconstituted, using aseptic technique, to 50 mg per mL as follows:

1. To minimize foaming, AVOID vigorous agitation or shaking of the vial during or after reconstitution.
2. Remove the polypropylene flip-off cap from the Daptomycin for Injection vial to expose the central portion of the rubber stopper.
3. Wipe the top of the rubber stopper with an alcohol swab or other antiseptic solution and allow to dry. After cleaning, do not touch the rubber stopper or allow it to touch any other surface.
4. Slowly transfer 7 mL of 0.9% sodium chloride injection through the center of the rubber stopper into the Daptomycin for Injection vial, pointing the transfer needle toward the wall of the vial. It is recommended that a beveled sterile transfer needle that is 21 gauge or smaller in diameter, or a needleless device is used, pointing the transfer needle toward the wall of the vial.
5. Ensure that all of the Daptomycin for Injection powder is wetted by gently rotating the vial.
  1. Allow the wetted product to stand undisturbed for 10 minutes.
  2. Gently rotate or swirl the vial contents for a few minutes, as needed, to obtain a completely reconstituted solution.

Administration Instructions

Parenteral drug products should be inspected visually for particulate matter prior to administration.

Slowly remove reconstituted liquid (50 mg daptomycin per mL) from the vial using a beveled sterile needle that is 21 gauge or smaller in diameter. Administer as an intravenous injection or infusion as described below:

Adults

Intravenous Injection over a period of 2 minutes

- For intravenous (IV) injection over a period of 2 minutes in adult patients only:Administer the appropriate volume of the reconstituted Daptomycin for Injection (concentration of 50 mg per mL).

Intravenous Infusion over a period of 30 minutes

- For intravenous (IV) infusion over a period of 30 minutes in adult patients: The appropriate volume of the reconstituted Daptomycin for Injection (concentration of 50 mg per mL) should be further diluted, using aseptic technique, into a 50 mL IV infusion bag containing 0.9% sodium chloride injection.

Pediatric Patients (1 to 17 Years of Age)

Intravenous Infusion over a period of 30 or 60 minutes

- Unlike in Adults, do NOT administer Daptomycin for Injection by injection over a two (2) minute period to pediatric patients [see Dosage and Administration (2.1)].
- For Intravenous infusion over a period of 60 minutes in pediatric patients 1 to 6 years of age: The appropriate volume of the reconstituted Daptomycin for Injection (concentration of 50 mg per mL) should be further diluted, using aseptic technique, into an intravenous infusion bag containing 25 mL of 0.9% sodium chloride injection. The infusion rate should be maintained at 0.42 mL/minute over the 60-minute period.
- For Intravenous infusion over a period of 30 minutes in pediatric patients 7 to 17 years of age: The appropriate volume of the reconstituted Daptomycin for Injection (concentration of 50 mg per mL) should be further diluted, using aseptic technique, into a 50 mL IV infusion bag containing 0.9% sodium chloride injection. The infusion rate should be maintained at 1.67 mL/minute over the 30-minute period.

No preservative or bacteriostatic agent is present in this product. Aseptic technique must be used in the preparation of final IV solution. Do not exceed the In-Use storage conditions of the reconstituted and diluted solutions of Daptomycin for Injection described below. Discard unused portions of daptomycin for injection.

In-Use Storage Conditions for Daptomycin for Injection Once Reconstituted in Acceptable Intravenous Diluents

Stability studies have shown that the reconstituted solution is stable in the vial for 12 hours at room temperature and up to 48 hours if stored under refrigeration between 2° and 8°C (36° and 46°F).

The diluted solution is stable in the infusion bag for 12 hours at room temperature and 48 hours if stored under refrigeration. The combined storage time (reconstituted solution in vial and diluted solution in infusion bag) should not exceed 12 hours at room temperature or 48 hours under refrigeration.

2.8 Compatible Intravenous Solutions

Daptomycin for Injection is compatible with 0.9% sodium chloride injection and Lactated Ringer's injection.

2.9 Incompatibilities

Daptomycin for Injection is not compatible with dextrose-containing diluents.

Daptomycin for Injection should not be used in conjunction with ReadyMED® elastomeric infusion pumps. Stability studies of daptomycin for injection solutions stored in ReadyMED® elastomeric infusion pumps identified an impurity (2-mercaptobenzothiazole) leaching from this pump system into the Daptomycin for Injection solution.

Because only limited data are available on the compatibility of daptomycin for injection with other IV substances, additives and other medications should not be added to Daptomycin for Injection single-dose vials or infusion bags, or infused simultaneously with Daptomycin for Injection through the same IV line. If the same IV line is used for sequential infusion of different drugs, the line should be flushed with a compatible intravenous solution before and after infusion with Daptomycin for Injection.

3 DOSAGE FORMS AND STRENGTHS

For Injection: 350 mg daptomycin as a sterile, pale yellow to light brown lyophilized powder for reconstitution in a single-dose vial.

4 CONTRAINDICATIONS

Daptomycin for injection is contraindicated in patients with known hypersensitivity to daptomycin [see Warnings and Precautions (5.1)].

5 WARNINGS AND PRECAUTIONS

5.1 Anaphylaxis/Hypersensitivity Reactions

Anaphylaxis/hypersensitivity reactions have been reported with the use of antibacterial agents, including daptomycin for injection, and may be life-threatening. If an allergic reaction to Daptomycin for Injection occurs, discontinue the drug and institute appropriate therapy [see Adverse Reactions (6.2)].

5.2 Myopathy and Rhabdomyolysis

Myopathy, defined as muscle aching or muscle weakness in conjunction with increases in creatine phosphokinase (CPK) values to greater than 10 times the upper limit of normal (ULN), has been reported with the use of daptomycin. Rhabdomyolysis, with or without acute renal failure, has been reported [see Adverse Reactions (6.2)].

Patients receiving Daptomycin for Injection should be monitored for the development of muscle pain or weakness, particularly of the distal extremities. In patients who receive Daptomycin for Injection, CPK levels should be monitored weekly, and more frequently in patients who received recent prior or concomitant therapy with an HMG-CoA reductase inhibitor or in whom elevations in CPK occur during treatment with Daptomycin for Injection.

In adult patients with renal impairment, both renal function and CPK should be monitored more frequently than once weekly [see Use in Specific Populations (8.6) and Clinical Pharmacology (12.3)].

In Phase 1 studies and Phase 2 clinical trials in adults, CPK elevations appeared to be more frequent when daptomycin was dosed more than once daily. Therefore, daptomycin should not be dosed more frequently than once a day.

Daptomycin should be discontinued in patients with unexplained signs and symptoms of myopathy in conjunction with CPK elevations to levels >1,000 U/L (~5× ULN), and in patients without reported symptoms who have marked elevations in CPK, with levels >2,000 U/L (≥10× ULN). In addition, consideration should be given to suspending agents associated with rhabdomyolysis, such as HMG-CoA reductase inhibitors, temporarily in patients receiving daptomycin [see Drug Interactions (7.1)].

5.3 Eosinophilic Pneumonia

Eosinophilic pneumonia has been reported in patients receiving daptomycin [see Adverse Reactions (6.2)]. In reported cases associated with daptomycin, patients developed fever, dyspnea with hypoxic respiratory insufficiency, and diffuse pulmonary infiltrates or organizing pneumonia. In general, patients developed eosinophilic pneumonia 2 to 4 weeks after starting daptomycin and improved when daptomycin was discontinued and steroid therapy was initiated. Recurrence of eosinophilic pneumonia upon re-exposure has been reported. Patients who develop these signs and symptoms while receiving daptomycin should undergo prompt medical evaluation, and daptomycin should be discontinued immediately. Treatment with systemic steroids is recommended.

5.4 Drug Reaction with Eosinophilia and Systemic Symptoms (DRESS)

DRESS has been reported in post-marketing experience with daptomycin [see Adverse Reactions (6.2)]. Patients who develop skin rash, fever, peripheral eosinophilia, and systemic organ (for example, hepatic, renal, pulmonary) impairment while receiving daptomycin should undergo medical evaluation. If DRESS is suspected, discontinue daptomycin promptly and institute appropriate treatment.

5.5 Tubulointerstitial Nephritis (TIN)

TIN has been reported in post-marketing experience with daptomycin [see Adverse Reactions (6.2)]. Patients who develop new or worsening renal impairment while receiving daptomycin should undergo medical evaluation. If TIN is suspected, discontinue daptomycin promptly and institute appropriate treatment.

5.6 Peripheral Neuropathy

Cases of peripheral neuropathy have been reported during the daptomycin postmarketing experience [see Adverse Reactions (6.2)]. Therefore, physicians should be alert to signs and symptoms of peripheral neuropathy in patients receiving daptomycin. Monitor for neuropathy and consider discontinuation.

5.7 Potential Nervous System and/or Muscular System Effects in Pediatric Patients Younger than 12 Months

Avoid use of daptomycin in pediatric patients younger than 12 months due to the risk of potential effects on muscular, neuromuscular, and/or nervous systems (either peripheral and/or central) observed in neonatal dogs with intravenous daptomycin [see Nonclinical Toxicology (13.2)].

5.8 Clostridioides difficile–Associated Diarrhea

Clostridioides difficile–associated diarrhea (CDAD) has been reported with the use of nearly all systemic antibacterial agents, including daptomycin, and may range in severity from mild diarrhea to fatal colitis [see Adverse Reactions (6.2)]. Treatment with antibacterial agents alters the normal flora of the colon, leading to overgrowth of C. difficile.

C. difficile produces toxins A and B, which contribute to the development of CDAD. Hypertoxin-producing strains of C. difficile cause increased morbidity and mortality, since these infections can be refractory to antimicrobial therapy and may require colectomy. CDAD must be considered in all patients who present with diarrhea following antibacterial use. Careful medical history is necessary because CDAD has been reported to occur more than 2 months after the administration of antibacterial agents.

If CDAD is suspected or confirmed, ongoing antibacterial use not directed against C. difficile may need to be discontinued. Appropriate fluid and electrolyte management, protein supplementation, antibacterial treatment of C. difficile, and surgical evaluation should be instituted as clinically indicated.

5.9 Persisting or Relapsing S. aureus Bacteremia/Endocarditis

Patients with persisting or relapsing S. aureus bacteremia/endocarditis or poor clinical response should have repeat blood cultures. If a blood culture is positive for S. aureus, minimum inhibitory concentration (MIC) susceptibility testing of the isolate should be performed using a standardized procedure, and diagnostic evaluation of the patient should be performed to rule out sequestered foci of infection. Appropriate surgical intervention (e.g., debridement, removal of prosthetic devices, valve replacement surgery) and/or consideration of a change in antibacterial regimen may be required.

Failure of treatment due to persisting or relapsing S. aureus bacteremia/endocarditis may be due to reduced daptomycin susceptibility (as evidenced by increasing MIC of the S. aureus isolate) [see Clinical Studies (14.2)].

5.10 Decreased Efficacy in Patients with Moderate Baseline Renal Impairment

Limited data are available from the two Phase 3 complicated skin and skin structure infection (cSSSI) trials regarding clinical efficacy of daptomycin treatment in adult patients with creatinine clearance (CLCR) <50 mL/min; only 31/534 (6%) patients treated with daptomycin in the intent-to-treat (ITT) population had a baseline CLCR <50 mL/min. Table 4 shows the number of adult patients by renal function and treatment group who were clinical successes in the Phase 3 cSSSI trials.

Table 4: Clinical Success Rates by Renal Function and Treatment Group in Phase 3 cSSSI Trials in Adult Patients (Population: ITT)
CLCR | Success Rate n/N (%)
CLCR | Daptomycin 4 mg/kg every 24h | Comparator
50 to 70 mL/min | 25/38 (66%) | 30/48 (63%)
30 to <50 mL/min | 7/15 (47%) | 20/35 (57%)

In a subgroup analysis of the ITT population in the Phase 3 S. aureus bacteremia/endocarditis trial, clinical success rates, as determined by a treatment-blinded Adjudication Committee [see Clinical Studies (14.2)], in the daptomycin-treated adult patients were lower in patients with baseline CLCR <50 mL/min (see Table 5). A decrease of the magnitude shown in Table 5 was not observed in comparator-treated patients.

Table 5: Adjudication Committee Clinical Success Rates at Test of Cure by Baseline Creatinine Clearance and Treatment Subgroup in the S. aureus Bacteremia/Endocarditis Trial in Adult Patients (Population: ITT)
Baseline CLCR | Success Rate n/N (%)
Baseline CLCR | Daptomycin 6 mg/kg every 24h |  | Comparator
Baseline CLCR | Bacteremia | Right-Sided Infective Endocarditis | Bacteremia | Right-Sided Infective Endocarditis
>80 mL/min | 30/50 (60%) | 7/14 (50%) | 19/42 (45%) | 5/11 (46%)
50 to 80 mL/min | 12/26 (46%) | 1/4 (25%) | 13/31 (42%) | 1/2 (50%)
30 to <50 mL/min | 2/14 (14%) | 0/1 (0%) | 7/17 (41%) | 1/1 (100%)

Consider these data when selecting antibacterial therapy for use in adult patients with baseline moderate to severe renal impairment.

5.11 Increased International Normalized Ratio (INR)/Prolonged Prothrombin Time

Clinically relevant plasma concentrations of daptomycin have been observed to cause a significant concentration-dependent false prolongation of prothrombin time (PT) and elevation of International Normalized Ratio (INR) when certain recombinant thromboplastin reagents are utilized for the assay [see Drug Interactions (7.2)].

5.12 Development of Drug-Resistant Bacteria

Prescribing Daptomycin for Injection in the absence of a proven or strongly suspected bacterial infection or a prophylactic indication is unlikely to provide benefit to the patient and increases the risk of the development of drug-resistant bacteria.

6 ADVERSE REACTIONS

The following adverse reactions are described, or described in greater detail, in other sections:

- Anaphylaxis/Hypersensitivity Reactions [see Warnings and Precautions (5.1)]
- Myopathy and Rhabdomyolysis [see Warnings and Precautions (5.2)]
- Eosinophilic Pneumonia [see Warnings and Precautions (5.3)]
- Drug Reaction with Eosinophilia and Systemic Symptoms [see Warnings and Precautions (5.4)]
- Tubulointerstitial Nephritis [see Warnings and Precautions (5.5)]
- Peripheral Neuropathy [see Warnings and Precautions (5.6)]
- Increased International Normalized Ratio (INR)/Prolonged Prothrombin Time [see Warnings and Precautions (5.11) and Drug Interactions (7.2)]

6.1 Clinical Trials Experience

Because clinical trials are conducted under widely varying conditions, adverse reaction rates observed in the clinical trials of a drug cannot be directly compared with rates in the clinical trials of another drug and may not reflect the rates observed in practice.

Clinical Trial Experience in Adult Patients

Clinical trials enrolled 1,864 adult patients treated with daptomycin and 1,416 treated with comparator.

Complicated Skin and Skin Structure Infection Trials in Adults

In Phase 3 complicated skin and skin structure infection (cSSSI) trials in adult patients, daptomycin was discontinued in 15/534 (2.8%) patients due to an adverse reaction, while comparator was discontinued in 17/558 (3.0%) patients.

The rates of the most common adverse reactions, organized by body system, observed in adult patients with cSSSI (receiving 4 mg/kg daptomycin) are displayed in Table 6.

Table 6: Incidence of Adverse Reactions that Occurred in ≥2% of Adult Patients in the Daptomycin Treatment Group and ≥ the Comparator Treatment Group in Phase 3 cSSSI Trials
Adverse Reaction | Adult Patients (%)
Adverse Reaction | Daptomycin 4 mg/kg (N=534) | Comparator* (N=558)
Gastrointestinal disorders
Diarrhea | 5.2 | 4.3
Nervous system disorders
Headache | 5.4 | 5.4
Dizziness | 2.2 | 2.0
Skin/subcutaneous disorders
Rash | 4.3 | 3.8
Diagnostic investigations
Abnormal liver function tests | 3.0 | 1.6
Elevated CPK | 2.8 | 1.8
Infections
Urinary tract infections | 2.4 | 0.5
Vascular disorders
Hypotension | 2.4 | 1.4
Respiratory disorders
Dyspnea | 2.1 | 1.6
*Comparator: vancomycin (1 g IV q12h) or an anti-staphylococcal semi-synthetic penicillin (i.e., nafcillin, oxacillin, cloxacillin, or flucloxacillin; 4 to 12 g/day IV in divided doses).

Drug-related adverse reactions (possibly or probably drug-related) that occurred in <1% of adult patients receiving daptomycin in the cSSSI trials are as follows:

Body as a Whole: fatigue, weakness, rigors, flushing, hypersensitivity

Blood/Lymphatic System: leukocytosis, thrombocytopenia, thrombocytosis, eosinophilia, increased International Normalized Ratio (INR)

Cardiovascular System: supraventricular arrhythmia

Dermatologic System: eczema

Digestive System: abdominal distension, stomatitis, jaundice, increased serum lactate dehydrogenase

Metabolic/Nutritional System: hypomagnesemia, increased serum bicarbonate, electrolyte disturbance

Musculoskeletal System: myalgia, muscle cramps, muscle weakness, arthralgia

Nervous System: vertigo, mental status change, paresthesia

Special Senses: taste disturbance, eye irritation

S. aureus Bacteremia/Endocarditis Trial in Adults

In the S. aureus bacteremia/endocarditis trial involving adult patients, daptomycin was discontinued in 20/120 (16.7%) patients due to an adverse reaction, while comparator was discontinued in 21/116 (18.1%) patients.

Serious Gram-negative infections (including bloodstream infections) were reported in 10/120 (8.3%) daptomycin-treated patients and 0/115 comparator-treated patients. Comparator-treated patients received dual therapy that included initial gentamicin for 4 days. Infections were reported during treatment and during early and late follow-up. Gram-negative infections included cholangitis, alcoholic pancreatitis, sternal osteomyelitis/mediastinitis, bowel infarction, recurrent Crohn's disease, recurrent line sepsis, and recurrent urosepsis caused by a number of different Gram-negative bacteria.

The rates of the most common adverse reactions, organized by System Organ Class (SOC), observed in adult patients with S. aureus bacteremia/endocarditis (receiving 6 mg/kg daptomycin) are displayed in Table 7.

Table 7: Incidence of Adverse Reactions that Occurred in ≥5% of Adult Patients in the Daptomycin Treatment Group and ≥ the Comparator Treatment Group in the S. aureus Bacteremia/Endocarditis Trial
Adverse Reaction* | Adult Patients n (%)
Adverse Reaction* | Daptomycin 6 mg/kg (N=120) | Comparator† (N=116)
Infections and infestations
Sepsis NOS | 6 (5%) | 3 (3%)
Bacteremia | 6 (5%) | 0 (0%)
Gastrointestinal disorders
Abdominal pain NOS | 7 (6%) | 4 (3%)
General disorders and administration site conditions
Chest pain | 8 (7%) | 7 (6%)
Edema NOS | 8 (7%) | 5 (4%)
Respiratory, thoracic and mediastinal disorders
Pharyngolaryngeal pain | 10 (8%) | 2 (2%)
Skin and subcutaneous tissue disorders
Pruritus | 7 (6%) | 6 (5%)
Sweating increased | 6 (5%) | 0 (0%)
Psychiatric disorders
Insomnia | 11 (9%) | 8 (7%)
Investigations
Blood creatine phosphokinase increased | 8 (7%) | 1 (1%)
Vascular disorders
Hypertension NOS | 7 (6%) | 3 (3%)
*NOS, not otherwise specified.
†Comparator: vancomycin (1 g IV q12h) or an anti-staphylococcal semi-synthetic penicillin (i.e., nafcillin, oxacillin, cloxacillin, or flucloxacillin; 2 g IV q4h), each with initial low-dose gentamicin.

The following reactions, not included above, were reported as possibly or probably drug-related in the daptomycin-treated group:

Blood and Lymphatic System Disorders: eosinophilia, lymphadenopathy, thrombocythemia, thrombocytopenia

Cardiac Disorders: atrial fibrillation, atrial flutter, cardiac arrest

Ear and Labyrinth Disorders: tinnitus

Eye Disorders: vision blurred

Gastrointestinal Disorders: dry mouth, epigastric discomfort, gingival pain, hypoesthesia oral

Infections and Infestations: candidal infection NOS, vaginal candidiasis, fungemia, oral candidiasis, urinary tract infection fungal

Investigations: blood phosphorous increased, blood alkaline phosphatase increased, INR increased, liver function test abnormal, alanine aminotransferase increased, aspartate aminotransferase increased, prothrombin time prolonged

Metabolism and Nutrition Disorders: appetite decreased NOS

Musculoskeletal and Connective Tissue Disorders: myalgia

Nervous System Disorders: dyskinesia, paresthesia

Psychiatric Disorders: hallucination NOS

Renal and Urinary Disorders: proteinuria, renal impairment NOS

Skin and Subcutaneous Tissue Disorders: pruritus generalized, rash vesicular

Other Trials in Adults

In Phase 3 trials of community-acquired pneumonia (CAP) in adult patients, the death rate and rates of serious cardiorespiratory adverse events were higher in daptomycin-treated patients than in comparator-treated patients. These differences were due to lack of therapeutic effectiveness of daptomycin in the treatment of CAP in patients experiencing these adverse events [see Indications and Usage (1.4)].

Laboratory Changes in Adults

Complicated Skin and Skin Structure Infection Trials in Adults

In Phase 3 cSSSI trials of adult patients receiving daptomycin at a dose of 4 mg/kg, elevations in CPK were reported as clinical adverse events in 15/534 (2.8%) daptomycin-treated patients, compared with 10/558 (1.8%) comparator-treated patients. Of the 534 patients treated with daptomycin, 1 (0.2%) had symptoms of muscle pain or weakness associated with CPK elevations to greater than 4 times the upper limit of normal (ULN). The symptoms resolved within 3 days and CPK returned to normal within 7 to 10 days after treatment was discontinued [see Warnings and Precautions (5.2)]. Table 8 summarizes the CPK shifts from Baseline through End of Therapy in the cSSSI adult trials.

Table 8: Incidence of CPK Elevations from Baseline during Therapy in Either the Daptomycin Treatment Group or the Comparator Treatment Group in Phase 3 cSSSI Adult Trials
Change in CPK |  | All Adult Patients |  |  |  | Adult Patients with Normal CPK at Baseline
Change in CPK |  | Daptomycin 4 mg/kg (N=430) |  | Comparator* (N=459) |  | Daptomycin 4 mg/kg (N=374) |  | Comparator* (N=392)
Change in CPK |  | % | n | % | n | % | n | % | n
No Increase |  | 90.7 | 390 | 91.1 | 418 | 91.2 | 341 | 91.1 | 357
Maximum Value | >1× ULN† | 9.3 | 40 | 8.9 | 41 | 8.8 | 33 | 8.9 | 35
 | >2× ULN | 4.9 | 21 | 4.8 | 22 | 3.7 | 14 | 3.1 | 12
 | >4× ULN | 1.4 | 6 | 1.5 | 7 | 1.1 | 4 | 1.0 | 4
 | >5× ULN | 1.4 | 6 | 0.4 | 2 | 1.1 | 4 | 0.0 | 0
 | >10× ULN | 0.5 | 2 | 0.2 | 1 | 0.2 | 1 | 0.0 | 0
Note: Elevations in CPK observed in adult patients treated with daptomycin or comparator were not clinically or statistically significantly different.
*Comparator: vancomycin (1 g IV q12h) or an anti-staphylococcal semi-synthetic penicillin (i.e., nafcillin, oxacillin, cloxacillin, or flucloxacillin; 4 to 12 g/day IV in divided doses).
† ULN (Upper Limit of Normal) is defined as 200 U/L.

S. aureus Bacteremia/Endocarditis Trial in Adults

In the S. aureus bacteremia/endocarditis trial in adult patients, at a dose of 6 mg/kg, 11/120 (9.2%) daptomycin-treated patients, including two patients with baseline CPK levels >500 U/L, had CPK elevations to levels >500 U/L, compared with 1/116 (0.9%) comparator-treated patients. Of the 11 daptomycin-treated patients, 4 had prior or concomitant treatment with an HMG-CoA reductase inhibitor. Three of these 11 daptomycin-treated patients discontinued therapy due to CPK elevation, while the one comparator-treated patient did not discontinue therapy [see Warnings and Precautions (5.2)].

Clinical Trial Experience in Pediatric Patients

Complicated Skin and Skin Structure Infection Trial in Pediatric Patients

The safety of daptomycin was evaluated in one clinical trial (in cSSSI), which included 256 pediatric patients (1 to 17 years of age) treated with intravenous daptomycin and 133 patients treated with comparator agents. Patients were given age-dependent doses once daily for a treatment period of up to 14 days (median treatment period was 3 days). The doses given by age group were as follows: 10 mg/kg for 1 to < 2 years, 9 mg/kg for 2 to 6 years, 7 mg/kg for 7 to 11 years and 5 mg/kg for 12 to 17 years of age [see Clinical Studies (14)]. Patients treated with daptomycin were (51%) male, (49%) female and (46%) Caucasian and (32%) Asian.

Adverse Reactions Leading to Discontinuation

In the cSSSI study, daptomycin was discontinued in 7/256 (2.7%) patients due to an adverse reaction, while comparator was discontinued in 7/133 (5.3%) patients.

Most Common Adverse Reactions

The rates of the most common adverse reactions, organized by body system, observed in these pediatric patients with cSSSI are displayed in Table 9.

Table 9: Adverse Reactions that Occurred in ≥2% of Pediatric Patients in the Daptomycin Treatment-Arm and Greater Than or Equal to the Comparator Treatment-Arm in the cSSSI Pediatric Trial
Adverse Reaction | Daptomycin (N = 256) | Comparator* (N = 133)
Adverse Reaction | n (%) | n (%)
Gastrointestinal disorders
Diarrhea | 18 (7.0) | 7 (5.3)
Vomiting | 7 (2.7) | 1 (0.8)
Abdominal Pain | 5 (2.0) | 0
Skin and subcutaneous tissue disorders
Pruritus | 8 (3.1) | 2 (1.5)
General disorders and administration site conditions
Pyrexia | 10 (3.9) | 4 (3.0)
Investigations
Blood CPK increased | 14 (5.5) | 7 (5.3)
Nervous system disorders
Headache | 7 (2.7) | 3 (2.3)
*Comparators included intravenous therapy with either vancomycin, clindamycin, or an anti-staphylococcal semi-synthetic penicillin (nafcillin, oxacillin or cloxacillin)

The safety profile in the clinical trial of cSSSI pediatric patients was similar to that observed in the cSSSI adult patients.

S. aureus Bacteremia Trial in Pediatric Patients

The safety of daptomycin was evaluated in one clinical trial (in S. aureus bacteremia), which treated 55 pediatric patients with intravenous daptomycin and 26 patients with comparator agents. Patients were given age-dependent doses once daily for a treatment period of up to 42 days (mean duration of IV treatment was 12 days). The doses by age group were as follows: 12 mg/kg for 1 to <6 years, 9 mg/kg for 7 to 11 years and 7 mg/kg for 12 to 17 years of age [see Clinical Studies (14)]. Patients treated with daptomycin were (69%) male and (31%) female. No patients 1 to <2 years of age were enrolled.

Adverse Reactions Leading to Discontinuation

In the bacteremia study, daptomycin was discontinued in 3/55 (5.5%) patients due to an adverse reaction, while comparator was discontinued in 2/26 (7.7%) patients.

Most Common Adverse Reactions

The rates of the most common adverse reactions, organized by body system, observed in these pediatric patients with bacteremia are displayed in Table 10.

Table 10: Incidence of Adverse Reactions that Occurred in ≥5% of Pediatric Patients in the Daptomycin Treatment-Arm and Greater Than or Equal to the Comparator Treatment-Arm in the Pediatric Bacteremia Trial
Adverse Reaction | Daptomycin (N = 55) | Comparator (N = 26)
Adverse Reaction | n (%) | n (%)
Gastrointestinal disorders
Vomiting | 6 (10.9) | 2 (7.7)
Investigations
Blood CPK increased | 4 (7.3) | 0
*Comparators included intravenous therapy with either vancomycin, cefazolin, or an anti-staphylococcal semi-synthetic penicillin (nafcillin, oxacillin or cloxacillin)

6.2 Post-Marketing Experience

The following adverse reactions have been identified during post-approval use of daptomycin. Because these reactions are reported voluntarily from a population of uncertain size, it is not always possible to reliably estimate their frequency or establish a causal relationship to drug exposure.

Blood and Lymphatic System Disorders: anemia, thrombocytopenia

General and Administration Site Conditions: pyrexia

Immune System Disorders: anaphylaxis; hypersensitivity reactions, including angioedema, pruritus, hives, shortness of breath, difficulty swallowing, truncal erythema, and pulmonary eosinophilia [see Contraindications (4) and Warnings and Precautions (5.1)]

Infections and Infestations: Clostridioides difficile–associated diarrhea [see Warnings and Precautions (5.8)]

Laboratory Investigations: platelet count decreased

Musculoskeletal Disorders: myoglobin increased; rhabdomyolysis (some reports involved patients treated concurrently with daptomycin and HMG-CoA reductase inhibitors) [see Warnings and Precautions (5.2), Drug Interactions (7.1), and Clinical Pharmacology (12.3)]

Respiratory, Thoracic, and Mediastinal Disorders: cough, eosinophilic pneumonia, organizing pneumonia [see Warnings and Precautions (5.3)]

Nervous System Disorders: peripheral neuropathy [see Warnings and Precautions (5.6)]

Skin and Subcutaneous Tissue Disorders: serious skin reactions, including drug reaction with eosinophilia and systemic symptoms (DRESS), vesiculobullous rash (with or without mucous membrane involvement, including Stevens-Johnson syndrome [SJS] and toxic epidermal necrolysis [TEN]), and acute generalized exanthematous pustulosis [see Warnings and Precautions (5.4)]

Gastrointestinal Disorders: nausea, vomiting

Renal and Urinary Disorders: acute kidney injury, renal insufficiency, renal failure, and tubulointerstitial nephritis (TIN) [see Warnings and Precautions (5.5)]

Special Senses: visual disturbances

7 DRUG INTERACTIONS

7.1 HMG-CoA Reductase Inhibitors

In healthy adult subjects, concomitant administration of daptomycin and simvastatin had no effect on plasma trough concentrations of simvastatin, and there were no reports of skeletal myopathy [see Clinical Pharmacology (12.3)].

However, inhibitors of HMG-CoA reductase may cause myopathy, which is manifested as muscle pain or weakness associated with elevated levels of creatine phosphokinase (CPK). In the adult Phase 3 S. aureus bacteremia/endocarditis trial, some patients who received prior or concomitant treatment with an HMG-CoA reductase inhibitor developed elevated CPK [see Adverse Reactions (6.1)]. Experience with the coadministration of HMG-CoA reductase inhibitors and daptomycin in patients is limited; therefore, consideration should be given to suspending use of HMG-CoA reductase inhibitors temporarily in patients receiving daptomycin.

7.2 Drug-Laboratory Test Interactions

Clinically relevant plasma concentrations of daptomycin have been observed to cause a significant concentration-dependent false prolongation of prothrombin time (PT) and elevation of International Normalized Ratio (INR) when certain recombinant thromboplastin reagents are utilized for the assay. The possibility of an erroneously elevated PT/INR result due to interaction with a recombinant thromboplastin reagent may be minimized by drawing specimens for PT or INR testing near the time of trough plasma concentrations of daptomycin. However, sufficient daptomycin concentrations may be present at trough to cause interaction.

If confronted with an abnormally high PT/INR result in a patient being treated with daptomycin, it is recommended that clinicians:

1. Repeat the assessment of PT/INR, requesting that the specimen be drawn just prior to the next daptomycin dose (i.e., at trough concentration). If the PT/INR value obtained at trough remains substantially elevated above what would otherwise be expected, consider evaluating PT/INR utilizing an alternative method.
2. Evaluate for other causes of abnormally elevated PT/INR results.

8 USE IN SPECIFIC POPULATIONS

8.1 Pregnancy

Risk Summary

Limited published data on use of daptomycin in pregnant women are insufficient to inform a drug-associated risk for major birth defects and miscarriage. In animal reproduction studies performed in rats and rabbits daptomycin was administered intravenously during organogenesis at doses 2 and 4-times, respectively, the recommended 6 mg/kg human dose (on a body surface area basis). No evidence of adverse developmental outcomes was observed.

The background risk of major birth defects and miscarriage for the indicated population is unknown. All pregnancies have a background risk of birth defect, loss, or other adverse outcomes. In the U.S. general population, the estimated background risk of major birth defects and miscarriage in clinically recognized pregnancies is 2 to 4% and 15 to 20%, respectively.

Data

Animal Data

In pregnant rats, daptomycin was administered intravenously at doses of 5, 20, or 75 mg/kg/day during the gestation days 6 to 18. Maternal body weight gain was decreased at 75 mg/kg/day.

No embryo/fetal effects were noted at the highest dose of 75 mg/kg/day, a dose approximately 2-fold higher than in humans at the recommended maximum dose of 6 mg/kg (based on body surface area).

In pregnant rabbits, daptomycin was administered intravenously at doses of 5, 20, or 75 mg/kg/day during the gestation days 6 to 15. Maternal body weight gain and food consumption were decreased at 75 mg/kg/day. No embryo/fetal effects were noted at the highest dose of 75 mg/kg/day, a dose approximately 4-fold higher than in humans at the maximum recommended dose of 6 mg/kg (based on body surface area).

In a combined fertility and pre/postnatal development study, daptomycin was administered intravenously to female rats at doses of 2, 25, 75 mg/kg/day from 14-days pre-mating through lactation/postpartum day 20). No effects on pre/postnatal development were observed up to the highest dose of 75 mg/kg/day, a dose approximately 2-fold higher than the maximum recommended human dose of 6 mg/kg (based on body surface area)^1.

8.2 Lactation

Risk Summary

Limited published data report that daptomycin is present in human milk at infant doses of 0.1% of the maternal dose (see Data)^2,3,4. There is no information on the effects of daptomycin on the breastfed infant or the effects of daptomycin on milk production. The developmental and health benefits of breastfeeding should be considered along with the mother's clinical need for daptomycin and any potential adverse effects on the breastfed infant from daptomycin or from the underlying maternal condition.

8.4 Pediatric Use

The safety and effectiveness of daptomycin in the treatment of cSSSI and S. aureus bloodstream infections (bacteremia) have been established in the age groups 1 to 17 years of age. Use of daptomycin in these age groups is supported by evidence from adequate and well-controlled studies in adults, with additional data from pharmacokinetic studies in pediatric patients, and from safety, efficacy and PK studies in pediatric patients with cSSSI and S. aureus bloodstream infections [see Adverse Reactions (6.1), Clinical Pharmacology (12.3), and Clinical Studies (14.1, 14.2)].

Safety and effectiveness in pediatric patients below the age of one year have not been established. Avoid use of daptomycin in pediatric patients younger than one year of age due to the risk of potential effects on muscular, neuromuscular, and/or nervous systems (either peripheral and/or central) observed in neonatal dogs [see Warnings and Precautions (5.7) and Nonclinical Toxicology (13.2)].

Daptomycin is not indicated in pediatric patients with renal impairment because dosage has not been established in these patients.

Daptomycin has not been studied in pediatric patients with other bacterial infections.

8.5 Geriatric Use

Of the 534 adult patients treated with daptomycin in Phase 3 controlled clinical trials of complicated skin and skin structure infections (cSSSI), 27% were 65 years of age or older and 12% were 75 years of age or older. Of the 120 adult patients treated with daptomycin in the Phase 3 controlled clinical trial of S. aureus bacteremia/endocarditis, 25% were 65 years of age or older and 16% were 75 years of age or older. In Phase 3 adult clinical trials of cSSSI and S. aureus bacteremia/endocarditis, clinical success rates were lower in patients ≥65 years of age than in patients <65 years of age. In addition, treatment-emergent adverse events were more common in patients ≥65 years of age than in patients <65 years of age.

The exposure of daptomycin was higher in healthy elderly subjects than in healthy young adult subjects. However, no adjustment of daptomycin dosage is warranted for elderly patients with creatinine clearance (CLCR) ≥30 mL/min [see Dosage and Administration (2.6) and Clinical Pharmacology (12.3)].

8.6 Patients with Renal Impairment

Daptomycin is eliminated primarily by the kidneys; therefore, a modification of daptomycin dosage interval is recommended for adult patients with CLCR <30 mL/min, including patients receiving hemodialysis or continuous ambulatory peritoneal dialysis (CAPD). In adult patients with renal impairment, both renal function and creatine phosphokinase (CPK) should be monitored more frequently than once weekly [see Dosage and Administration (2.6), Warnings and Precautions (5.2, 5.10), and Clinical Pharmacology (12.3)].

The dosage regimen for daptomycin in pediatric patients with renal impairment has not been established.

10 OVERDOSAGE

In the event of overdosage, supportive care is advised with maintenance of glomerular filtration. Daptomycin is cleared slowly from the body by hemodialysis (approximately 15% of the administered dose is removed over 4 hours) and by peritoneal dialysis (approximately 11% of the administered dose is removed over 48 hours). The use of high-flux dialysis membranes during 4 hours of hemodialysis may increase the percentage of dose removed compared with that removed by low-flux membranes.

11 DESCRIPTION

Daptomycin for Injection contains daptomycin, a cyclic lipopeptide antibacterial agent derived from the fermentation of Streptomyces roseosporus. The chemical name is N-decanoyl-L-tryptophyl-D-asparaginyl-L-aspartyl-L-threonylglycyl-L-ornithyl-L-aspartyl-D-alanyl-L-aspartylglycyl-D-seryl-threo-3-methyl-L-glutamyl-3-anthraniloyl-L-alanine ε1-lactone. The chemical structure is:

The empirical formula is C72H101N17O26; the molecular weight is 1620.67. Daptomycin for Injection is supplied in a single-dose vial as a sterile, preservative-free, pale yellow to light brown, lyophilized cake containing approximately 350 mg of daptomycin for intravenous (IV) use following reconstitution with 0.9% sodium chloride injection [see Dosage and Administration (2.7)]. The only inactive ingredient is sodium hydroxide, which is used for pH adjustment; between 4.0 to 5.0. Freshly reconstituted solutions of Daptomycin for Injection range in color from pale yellow to light brown.

12 CLINICAL PHARMACOLOGY

12.1 Mechanism of Action

Daptomycin is an antibacterial drug [see Clinical Pharmacology (12.4)].

12.2 Pharmacodynamics

Based on animal models of infection, the antimicrobial activity of daptomycin appears to correlate with the AUC/MIC (area under the concentration-time curve/minimum inhibitory concentration) ratio for certain pathogens, including S. aureus. The principal pharmacokinetic/pharmacodynamic parameter best associated with clinical and microbiological cure has not been elucidated in clinical trials with daptomycin.

12.3 Pharmacokinetics

Daptomycin Administered over a 30-Minute Period in Adults

The mean and standard deviation (SD) pharmacokinetic parameters of daptomycin at steady-state following intravenous (IV) administration of daptomycin over a 30-minute period at 4 to 12 mg/kg every 24h to healthy young adults are summarized in Table 11.

Table 11: Mean (SD) Daptomycin Pharmacokinetic Parameters in Healthy Adult Volunteers at Steady-State
Dose*† (mg/kg) | Pharmacokinetic Parameters‡
Dose*† (mg/kg) | AUC 0-24 (mcg•h/mL) | t 1/2 (h) | Vss (L/kg) | CLT (mL/h/kg) | Cmax (mcg/mL)
4 (N=6) | 494 (75) | 8.1 (1.0) | 0.096 (0.009) | 8.3 (1.3) | 57.8 (3.0)
6 (N=6) | 632 (78) | 7.9 (1.0) | 0.101 (0.007) | 9.1 (1.5) | 93.9 (6.0)
8 (N=6) | 858 (213) | 8.3 (2.2) | 0.101 (0.013) | 9.0 (3.0) | 123.3 (16.0)
10 (N=9) | 1039 (178) | 7.9 (0.6) | 0.098 (0.017) | 8.8 (2.2) | 141.1 (24.0)
12 (N=9) | 1277 (253) | 7.7 (1.1) | 0.097 (0.018) | 9.0 (2.8) | 183.7 (25.0)
*Daptomycin was administered by IV infusion over a 30-minute period.
†Doses of daptomycin in excess of 6 mg/kg have not been approved.
‡AUC0-24, area under the concentration-time curve from 0 to 24 hours; t1/2, elimination half-life; Vss, volume of distribution at steady-state; CLT, total plasma clearance; Cmax, maximum plasma concentration.

Daptomycin pharmacokinetics were generally linear and time-independent at daptomycin doses of 4 to 12 mg/kg every 24h administered by IV infusion over a 30-minute period for up to 14 days. Steady-state trough concentrations were achieved by the third daily dose. The mean (SD) steady-state trough concentrations attained following the administration of 4, 6, 8, 10, and 12 mg/kg every 24h were 5.9 (1.6), 6.7 (1.6), 10.3 (5.5), 12.9 (2.9), and 13.7 (5.2) mcg/mL, respectively.

Daptomycin Administered over a 2-Minute Period in Adults

Following IV administration of daptomycin over a 2-minute period to healthy adult volunteers at doses of 4 mg/kg (N=8) and 6 mg/kg (N=12), the mean (SD) steady-state systemic exposure (AUC) values were 475 (71) and 701 (82) mcg•h/mL, respectively. Values for maximum plasma concentration (Cmax) at the end of the 2-minute period could not be determined adequately in this study. However, using pharmacokinetic parameters from 14 healthy adult volunteers who received a single dose of daptomycin 6 mg/kg IV administered over a 30-minute period in a separate study, steady-state Cmax values were simulated for daptomycin 4 and 6 mg/kg IV administered over a 2-minute period. The simulated mean (SD) steady-state Cmax values were 77.7 (8.1) and 116.6 (12.2) mcg/mL, respectively.

Distribution

Daptomycin is reversibly bound to human plasma proteins, primarily to serum albumin, in a concentration-independent manner. The overall mean binding ranges from 90 to 93%.

In clinical studies, mean serum protein binding in adult subjects with creatinine clearance (CLCR) ≥30 mL/min was comparable to that observed in healthy adult subjects with normal renal function. However, there was a trend toward decreasing serum protein binding among subjects with CLCR <30 mL/min (88%), including those receiving hemodialysis (86%) and continuous ambulatory peritoneal dialysis (CAPD) (84%). The protein binding of daptomycin in adult subjects with moderate hepatic impairment (Child-Pugh Class B) was similar to that in healthy adult subjects.

The volume of distribution at steady-state (Vss) of daptomycin in healthy adult subjects was approximately 0.1 L/kg and was independent of dose.

Metabolism

In in vitro studies, daptomycin was not metabolized by human liver microsomes.

In 5 healthy adults after infusion of radiolabeled ^14C-daptomycin, the plasma total radioactivity was similar to the concentration determined by microbiological assay. Inactive metabolites were detected in urine, as determined by the difference between total radioactive concentrations and microbiologically active concentrations. In a separate study, no metabolites were observed in plasma on Day 1 following the administration of daptomycin at 6 mg/kg to adult subjects. Minor amounts of three oxidative metabolites and one unidentified compound were detected in urine. The site of metabolism has not been identified.

Excretion

Daptomycin is excreted primarily by the kidneys. In a mass balance study of 5 healthy adult subjects using radiolabeled daptomycin, approximately 78% of the administered dose was recovered from urine based on total radioactivity (approximately 52% of the dose based on microbiologically active concentrations), and 5.7% of the administered dose was recovered from feces (collected for up to 9 days) based on total radioactivity.

Specific Populations

Patients with Renal Impairment

Population-derived pharmacokinetic parameters were determined for infected adult patients (complicated skin and skin structure infections [cSSSI] and S. aureus bacteremia) and noninfected adult subjects with various degrees of renal function (Table 12). Total plasma clearance (CLT), elimination half-life (t1/2), and volume of distribution at steady-state (Vss) in patients with cSSSI were similar to those in patients with S. aureus bacteremia. Following administration of daptomycin 4 mg/kg every 24h by IV infusion over a 30-minute period, the mean CLT was 9%, 22%, and 46% lower among subjects and patients with mild (CLCR 50 to 80 mL/min), moderate (CLCR 30 to <50 mL/min), and severe (CLCR <30 mL/min) renal impairment, respectively, than in those with normal renal function (CLCR >80 mL/min). The mean steady-state systemic exposure (AUC), t1/2, and Vss increased with decreasing renal function, although the mean AUC for patients with CLCR 30 to 80 mL/min was not markedly different from the mean AUC for patients with normal renal function. The mean AUC for patients with CLCR <30 mL/min and for patients on dialysis (CAPD and hemodialysis dosed post-dialysis) was approximately 2 and 3 times higher, respectively, than for patients with normal renal function. The mean Cmax ranged from 60 to 70 mcg/mL in patients with CLCR ≥30 mL/min, while the mean Cmax for patients with CLCR <30 mL/min ranged from 41 to 58 mcg/mL. After administration of daptomycin 6 mg/kg every 24h by IV infusion over a 30-minute period, the mean Cmax ranged from 80 to 114 mcg/mL in patients with mild to moderate renal impairment and was similar to that of patients with normal renal function.

Table 12: Mean (SD) Daptomycin Population Pharmacokinetic Parameters Following Infusion of Daptomycin 4 mg/kg or 6 mg/kg to Infected Adult Patients and Noninfected Adult Subjects with Various Degrees of Renal Function
Renal Function | Pharmacokinetic Parameters*
Renal Function | t 1/2† (h) 4 mg/kg | Vss† (L/kg) 4 mg/kg | CLT† (mL/h/kg) 4 mg/kg | AUC 0-∞† (mcg•h/mL) 4 mg/kg | AUCss‡ (mcg•h/mL) 6 mg/kg | Cmin,ss‡ (mcg/mL) 6 mg/kg
Normal (CLCR >80 mL/min) | 9.39 (4.74) N=165 | 0.13 (0.05) N=165 | 10.9 (4.0) N=165 | 417 (155) N=165 | 545 (296) N=62 | 6.9 (3.5) N=61
Mild Renal Impairment (CLCR 50 to 80 mL/min) | 10.75 (8.36) N=64 | 0.12 (0.05) N=64 | 9.9 (4.0) N=64 | 466 (177) N=64 | 637 (215) N=29 | 12.4 (5.6) N=29
Moderate Renal Impairment (CLCR 30 to <50 mL/min) | 14.70 (10.50) N=24 | 0.15 (0.06) N=24 | 8.5 (3.4) N=24 | 560 (258) N=24 | 868 (349) N=15 | 19.0 (9.0) N=14
Severe Renal Impairment (CLCR <30 mL/min) | 27.83 (14.85) N=8 | 0.20 (0.15) N=8 | 5.9 (3.9) N=8 | 925 (467) N=8 | 1050 (892) N=2 | 24.4 (21.4) N=2
Hemodialysis | 30.51 (6.51) N=16 | 0.16 (0.04) N=16 | 3.9 (2.1) N=16 | 1193 (399) N=16 | NA | NA
CAPD | 27.56 (4.53) N=5 | 0.11 (0.02) N=5 | 2.9 (0.4) N=5 | 1409 (238) N=5 | NA | NA
Note: Daptomycin was administered over a 30-minute period.
*CLCR, creatinine clearance estimated using the Cockcroft-Gault equation with actual body weight; CAPD, continuous ambulatory peritoneal dialysis; AUC0-∞, area under the concentration-time curve extrapolated to infinity; AUCss, area under the concentration-time curve calculated over the 24-hour dosing interval at steady-state; Cmin,ss, trough concentration at steady-state; NA, not applicable.
†Parameters obtained following a single dose from patients with complicated skin and skin structure infections and healthy subjects.
‡Parameters obtained at steady-state from patients with S. aureus bacteremia.

Because renal excretion is the primary route of elimination, adjustment of daptomycin dosage interval is necessary in adult patients with severe renal impairment (CLCR <30 mL/min) [see Dosage and Administration (2.6)].

Patients with Hepatic Impairment

The pharmacokinetics of daptomycin were evaluated in 10 adult subjects with moderate hepatic impairment (Child-Pugh Class B) and compared with those in healthy adult volunteers (N=9) matched for gender, age, and weight. The pharmacokinetics of daptomycin were not altered in subjects with moderate hepatic impairment. No dosage adjustment is warranted when daptomycin is administered to patients with mild to moderate hepatic impairment. The pharmacokinetics of daptomycin in patients with severe hepatic impairment (Child-Pugh Class C) have not been evaluated.

Gender

No clinically significant gender-related differences in daptomycin pharmacokinetics have been observed. No dosage adjustment is warranted based on gender when daptomycin is administered.

Geriatric Patients

The pharmacokinetics of daptomycin were evaluated in 12 healthy elderly subjects (≥75 years of age) and 11 healthy young adult controls (18 to 30 years of age). Following administration of a single 4 mg/kg dose of daptomycin by IV infusion over a 30-minute period, the mean total clearance of daptomycin was approximately 35% lower and the mean AUC0-∞ was approximately 58% higher in elderly subjects than in healthy young adult subjects. There were no differences in Cmax [see Use in Specific Populations (8.5)].

Obese Patients

The pharmacokinetics of daptomycin were evaluated in 6 moderately obese (Body Mass Index [BMI] 25 to 39.9 kg/m^2) and 6 extremely obese (BMI ≥40 kg/m^2) adult subjects and controls matched for age, gender, and renal function. Following administration of daptomycin by IV infusion over a 30-minute period as a single 4 mg/kg dose based on total body weight, the total plasma clearance of daptomycin normalized to total body weight was approximately 15% lower in moderately obese subjects and 23% lower in extremely obese subjects than in nonobese controls. The AUC0-∞ of daptomycin was approximately 30% higher in moderately obese subjects and 31% higher in extremely obese subjects than in nonobese controls. The differences were most likely due to differences in the renal clearance of daptomycin. No adjustment of daptomycin dosage is warranted in obese patients.

Pediatric Patients

The pharmacokinetics of daptomycin in pediatric subjects was evaluated in 3 single-dose pharmacokinetic studies. In general, body weight-normalized total body clearance in pediatric patients was higher than in adults and increased with a decrease of age, whereas elimination half-life tends to decrease with a decrease of age. Body weight-normalized total body clearance and elimination half-life of daptomycin in children 2 to 6 years of age were similar at different doses.

A study was conducted to assess safety, efficacy, and pharmacokinetics of daptomycin in pediatric patients (1 to 17 years old, inclusive) with cSSSI caused by Gram-positive pathogens. Patients were enrolled into 4 age groups [see Clinical Studies (14.1)], and intravenous daptomycin doses of 5 to 10 mg/kg once daily were administered. Following administration of multiple doses, daptomycin exposure (AUCss and Cmax,ss) was similar across different age groups after dose adjustment based on body weight and age (Table 13).

Table 13: Mean (SD) Daptomycin Population Pharmacokinetic Parameters in cSSSI Pediatric Patients
Age | Pharmacokinetic Parameters
Age | Dose (mg/kg) | Infusion Duration (min) | AUCss (mcg•h/mL) | t 1/2 (h) | Vss (mL) | CLT (mL/h/kg) | Cmax,ss (mcg/mL)
12 to 17 years (N=6) | 5 | 30 | 434 (67.9) | 7.1 (0.9) | 8200 (3250) | 11.8 (2.15) | 76.4 (6.75)
7 to 11 years (N=2) | 7 | 30 | 543* | 6.8* | 4470* | 13.2* | 92.4*
2 to 6 years (N=7) | 9 | 60 | 452 (93.1) | 4.6 (0.8) | 2750 (832) | 20.8 (4.29) | 90.3 (14.0)
1 to less than 2 years (N=27) | 10 | 60 | 462 (138) | 4.8 (0.6) | 1670 (446) | 23.1 (5.43) | 81.6 (20.7)
AUCss, area under the concentration-time curve at steady state; CLT, clearance normalized to body weight; Vss, volume of distribution at steady state; t½, terminal half-life
*Mean is calculated from N=2

A study was conducted to assess safety, efficacy, and pharmacokinetics of daptomycin in pediatric patients with S. aureus bacteremia. Patients were enrolled into 3 age groups [see Clinical Studies (14.2)], and intravenous doses of 7 to 12 mg/kg once daily were administered. Following administration of multiple doses, daptomycin exposure (AUCss and Cmax,ss) was similar across different age groups after dose adjustment based on body weight and age (Table 14).

Table 14: Mean (SD) of Daptomycin Pharmacokinetics in Bacteremia Pediatric Patients
Age | Pharmacokinetic Parameters
Age | Dose (mg/kg) | Infusion Duration (min) | AUCss (mcg•h/mL) | t 1/2 (h) | Vss (mL) | CLT (mL/h/kg) | Cmax,ss (mcg/mL)
12 to 17 years (N=13) | 7 | 30 | 656 (334) | 7.5 (2.3) | 6420 (1980) | 12.4 (3.9) | 104 (35.5)
7 to 11 years (N=19) | 9 | 30 | 579 (116) | 6.0 (0.8) | 4510 (1470) | 15.9 (2.8) | 104 (14.5)
2 to 6 years (N=19) | 12 | 60 | 620 (109) | 5.1 (0.6) | 2200 (570) | 19.9 (3.4) | 106 (12.8)
AUCss, area under the concentration-time curve at steady state; CLT, clearance normalized to body weight; Vss, volume of distribution at steady state; t½, terminal half-life
No patients 1 to <2 years of age were enrolled in the study. Simulation using a population pharmacokinetic model demonstrated that the AUCss of daptomycin in pediatric patients 1 to <2 years of age receiving 12 mg/kg once daily would be comparable to that in adult patients receiving 6 mg/kg once daily.

Drug Interaction Studies

In Vitro Studies

In vitro studies with human hepatocytes indicate that daptomycin does not inhibit or induce the activities of the following human cytochrome P450 isoforms: 1A2, 2A6, 2C9, 2C19, 2D6, 2E1, and 3A4. It is unlikely that daptomycin will inhibit or induce the metabolism of drugs metabolized by the P450 system.

Aztreonam

In a study in which 15 healthy adult subjects received a single dose of daptomycin 6 mg/kg IV and a combination dose of daptomycin 6 mg/kg IV and aztreonam 1 g IV, administered over a 30-minute period, the Cmax and AUC0-∞ of daptomycin were not significantly altered by aztreonam.

Tobramycin

In a study in which 6 healthy adult males received a single dose of daptomycin 2 mg/kg IV, tobramycin 1 mg/kg IV, and both in combination, administered over a 30-minute period, the mean Cmax and AUC0-∞ of daptomycin were 12.7% and 8.7% higher, respectively, when daptomycin was coadministered with tobramycin. The mean Cmax and AUC0-∞ of tobramycin were 10.7% and 6.6% lower, respectively, when tobramycin was coadministered with daptomycin. These differences were not statistically significant. The interaction between daptomycin and tobramycin with a clinical dose of daptomycin is unknown.

Warfarin

In 16 healthy adult subjects, administration of daptomycin 6 mg/kg every 24h by IV infusion over a 30-minute period for 5 days, with coadministration of a single oral dose of warfarin (25 mg) on the 5th day, had no significant effect on the pharmacokinetics of either drug and did not significantly alter the INR (International Normalized Ratio).

Simvastatin

In 20 healthy adult subjects on a stable daily dose of simvastatin 40 mg, administration of daptomycin 4 mg/kg every 24h by IV infusion over a 30-minute period for 14 days (N=10) had no effect on plasma trough concentrations of simvastatin and was not associated with a higher incidence of adverse events, including skeletal myopathy, than in subjects receiving placebo once daily (N=10) [see Warnings and Precautions (5.2) and Drug Interactions (7.1)].

Probenecid

Concomitant administration of probenecid (500 mg 4 times daily) and a single dose of daptomycin 4 mg/kg by IV infusion over a 30-minute period in adults did not significantly alter the Cmax or AUC0-∞ of daptomycin.

12.4 Microbiology

Daptomycin belongs to the cyclic lipopeptide class of antibacterials. Daptomycin has clinical utility in the treatment of infections caused by aerobic, Gram-positive bacteria. The in vitro spectrum of activity of daptomycin encompasses most clinically relevant Gram-positive pathogenic bacteria.

Daptomycin exhibits rapid, concentration-dependent bactericidal activity against Gram-positive bacteria in vitro. This has been demonstrated both by time-kill curves and by MBC/MIC (minimum bactericidal concentration/minimum inhibitory concentration) ratios using broth dilution methodology. Daptomycin maintained bactericidal activity in vitro against stationary phase S. aureus in simulated endocardial vegetations. The clinical significance of this is not known.

Mechanism of Action

Daptomycin binds to bacterial cell membranes and causes a rapid depolarization of membrane potential. This loss of membrane potential causes inhibition of DNA, RNA, and protein synthesis, which results in bacterial cell death.

Resistance

The mechanism(s) of daptomycin resistance is not fully understood. Currently, there are no known transferable elements that confer resistance to daptomycin.

Interactions with Other Antibacterials

In vitro studies have investigated daptomycin interactions with other antibacterials. Antagonism, as determined by kill curve studies, has not been observed. In vitro synergistic interactions of daptomycin with aminoglycosides, β-lactam antibacterials, and rifampin have been shown against some isolates of staphylococci (including some methicillin-resistant isolates) and enterococci (including some vancomycin-resistant isolates).

Complicated Skin and Skin Structure Infection (cSSSI) Trials in Adults

The emergence of daptomycin non-susceptible isolates occurred in 2 infected patients across the set of Phase 2 and pivotal Phase 3 clinical trials of cSSSI in adult patients. In one case, a non-susceptible S. aureus was isolated from a patient in a Phase 2 trial who received daptomycin at less than the protocol-specified dose for the initial 5 days of therapy. In the second case, a non-susceptible Enterococcus faecalis was isolated from a patient with an infected chronic decubitus ulcer who was enrolled in a salvage trial.

S. aureus Bacteremia/Endocarditis and Other Post-Approval Trials in Adults

In subsequent clinical trials in adult patients, non-susceptible isolates were recovered. S. aureus was isolated from a patient in a compassionate-use trial and from 7 patients in the S. aureus bacteremia/endocarditis trial [see Clinical Studies (14.2)]. An E. faecium was isolated from a patient in a vancomycin-resistant enterococci trial.

Antimicrobial Activity

Daptomycin has been shown to be active against most isolates of the following microorganisms both in vitro and in clinical infections [see Indications and Usage (1)].

Gram-Positive Bacteria
Enterococcus faecalis (vancomycin-susceptible isolates only)
Staphylococcus aureus (including methicillin-resistant isolates)
Streptococcus agalactiae
Streptococcus dysgalactiae subsp. equisimilis
Streptococcus pyogenes

The following in vitro data are available, but their clinical significance is unknown. At least 90 percent of the following bacteria exhibit an in vitro minimum inhibitory concentration (MIC) less than or equal to the susceptible breakpoint for daptomycin against isolates of similar genus or organism group. However, the efficacy of daptomycin in treating clinical infections caused by these bacteria has not been established in adequate and well-controlled clinical trials.

Gram-Positive Bacteria
Corynebacterium jeikeium
Enterococcus faecalis (vancomycin-resistant isolates)
Enterococcus faecium (including vancomycin-resistant isolates)
Staphylococcus epidermidis (including methicillin-resistant isolates)
Staphylococcus haemolyticus

Susceptibility Testing

For specific information regarding susceptibility test interpretive criteria and associated test methods and quality control standards recognized by FDA for this drug, please see: https://www.fda.gov/STIC.

13 NONCLINICAL TOXICOLOGY

13.1 Carcinogenesis, Mutagenesis, Impairment of Fertility

Long-term carcinogenicity studies in animals have not been conducted to evaluate the carcinogenic potential of daptomycin. However, neither mutagenic nor clastogenic potential was found in a battery of genotoxicity tests, including the Ames assay, a mammalian cell gene mutation assay, a test for chromosomal aberrations in Chinese hamster ovary cells, an in vivo micronucleus assay, an in vitro DNA repair assay, and an in vivo sister chromatid exchange assay in Chinese hamsters.

Daptomycin did not affect the fertility or reproductive performance of male and female rats when administered intravenously at doses of 25, 75, or 150 mg/kg/day, which is approximately up to 9 times the estimated human exposure level based upon AUCs (or approximately up to 4 times the recommended human dose of 6 mg/kg based on body surface area comparison).

13.2 Animal Toxicology and/or Pharmacology

Adult Animals

In animals, daptomycin administration has been associated with effects on skeletal muscle. However, there were no changes in cardiac or smooth muscle. Skeletal muscle effects were characterized by microscopic degenerative/regenerative changes and variable elevations in creatine phosphokinase (CPK). No fibrosis or rhabdomyolysis was evident in repeat-dose studies up to the highest doses tested in rats (150 mg/kg/day) and dogs (100 mg/kg/day). The degree of skeletal myopathy showed no increase when treatment was extended from 1 month to up to 6 months. Severity was dose-dependent. All muscle effects, including microscopic changes, were fully reversible within 30 days following the cessation of dosing.

In adult animals, effects on peripheral nerve (characterized by axonal degeneration and frequently accompanied by significant losses of patellar reflex, gag reflex, and pain perception) were observed at daptomycin doses higher than those associated with skeletal myopathy. Deficits in the dogs' patellar reflexes were seen within 2 weeks after the start of treatment at 40 mg/kg/day (9 times the human Cmax at the 6 mg/kg/day dose), with some clinical improvement noted within 2 weeks after the cessation of dosing. However, at 75 mg/kg/day for 1 month, 7 of 8 dogs failed to regain full patellar reflex responses within a 3-month recovery period. In a separate study in dogs receiving doses of 75 and 100 mg/kg/day for 2 weeks, minimal residual histological changes were noted at 6 months after the cessation of dosing. However, recovery of peripheral nerve function was evident.

Tissue distribution studies in rats showed that daptomycin is retained in the kidney but appears to penetrate the blood-brain barrier only minimally following single and multiple doses.

Juvenile Animals

Target organs of daptomycin-related effects in 7-week-old juvenile dogs were skeletal muscle and nerve, the same target organs as in adult dogs. In juvenile dogs, nerve effects were noted at lower daptomycin blood concentrations than in adult dogs following 28 days of dosing. In contrast to adult dogs, juvenile dogs also showed evidence of effects in nerves of the spinal cord as well as peripheral nerves after 28 days of dosing. No nerve effects were noted in juvenile dogs following 14 days of dosing at doses up to 75 mg/kg/day.

Administration of daptomycin to 7-week-old juvenile dogs for 28 days at doses of 50 mg/kg/day produced minimal degenerative effects on the peripheral nerve and spinal cord in several animals, with no corresponding clinical signs. A dose of 150 mg/kg/day for 28 days produced minimal degeneration in the peripheral nerve and spinal cord as well as minimal to mild degeneration of the skeletal muscle in a majority of animals, accompanied by slight to severe muscle weakness evident in most dogs. Following a 28-day recovery phase, microscopic examination revealed recovery of the skeletal muscle and the ulnar nerve effects, but nerve degeneration in the sciatic nerve and spinal cord was still observed in all 150 mg/kg/day dogs.

Following once-daily administration of daptomycin to juvenile dogs for 28 days, microscopic effects in nerve tissue were noted at a Cmax value of 417 mcg/mL, which is approximately 3-fold less than the Cmax value associated with nerve effects in adult dogs treated once daily with daptomycin for 28 days (1308 mcg/mL).

Neonatal Animals

Neonatal dogs (4 to 31 days old) were more sensitive to daptomycin-related adverse nervous system and/or muscular system effects than either juvenile or adult dogs. In neonatal dogs, adverse nervous system and/or muscular system effects were associated with a Cmax value approximately 3-fold less than the Cmax in juvenile dogs, and 9-fold less than the Cmax in adult dogs following 28 days of dosing. At a dose of 25 mg/kg/day with associated Cmax and AUCinf values of 147 mcg/mL and 717 mcg•h/mL, respectively (1.6 and 1.0-fold the adult human Cmax and AUC, respectively, at the 6 mg/kg/day dose), mild clinical signs of twitching and one incidence of muscle rigidity were observed with no corresponding effect on body weight. These effects were found to be reversible within 28 days after treatment had stopped.

At higher dose levels of 50 and 75 mg/kg/day with associated Cmax and AUCinf values of ≥321 mcg/mL and ≥1470 mcg•h/mL, respectively, marked clinical signs of twitching, muscle rigidity in the limbs, and impaired use of limbs were observed. Resulting decreases in body weights and overall body condition at doses ≥50 mg/kg/day necessitated early discontinuation by postnatal day (PND) 19.

Histopathological assessment did not reveal any daptomycin-related changes in the peripheral and central nervous system tissue, as well as in the skeletal muscle or other tissues assessed, at any dose level.

No adverse effects were observed in the dogs that received daptomycin at 10 mg/kg/day, the NOAEL, with associated Cmax and AUCinf values of 62 mcg/mL and 247 mcg•h/mL, respectively (or 0.6 and 0.4-fold the adult human Cmax and AUC, respectively at the 6 mg/kg dose).

14 CLINICAL STUDIES

14.1 Complicated Skin and Skin Structure Infections

Adults with cSSSI

Adult patients with clinically documented complicated skin and skin structure infections (cSSSI) (Table 15) were enrolled in two randomized, multinational, multicenter, investigator-blinded trials comparing daptomycin (4 mg/kg IV every 24h) with either vancomycin (1 g IV every 12h) or an anti-staphylococcal semi-synthetic penicillin (i.e., nafcillin, oxacillin, cloxacillin, or flucloxacillin; 4 to 12 g IV per day). Patients could switch to oral therapy after a minimum of 4 days of IV treatment if clinical improvement was demonstrated. Patients known to have bacteremia at baseline were excluded. Patients with creatinine clearance (CLCR) between 30 and 70 mL/min were to receive a lower dose of daptomycin as specified in the protocol; however, the majority of patients in this subpopulation did not have the dose of daptomycin adjusted.

Table 15: Investigator's Primary Diagnosis in the cSSSI Trials in Adult Patients (Population: ITT)
Primary Diagnosis | Adult Patients (Daptomycin / Comparator*)
Primary Diagnosis | Study 9801 N=264 / N=266 | Study 9901 N=270 / N=292 | Pooled N=534 / N=558
Wound Infection | 99 (38%) / 116 (44%) | 102 (38%) / 108 (37%) | 201 (38%) / 224 (40%)
Major Abscess | 55 (21%) / 43 (16%) | 59 (22%) / 65 (22%) | 114 (21%) / 108 (19%)
Ulcer Infection | 71 (27%) / 75 (28%) | 53 (20%) / 68 (23%) | 124 (23%) / 143 (26%)
Other Infection† | 39 (15%) / 32 (12%) | 56 (21%) / 51 (18%) | 95 (18%) / 83 (15%)
*Comparator: vancomycin (1 g IV q12h) or an anti-staphylococcal semi-synthetic penicillin (i.e., nafcillin, oxacillin, cloxacillin, or flucloxacillin; 4 to 12 g/day IV in divided doses).
†The majority of cases were subsequently categorized as complicated cellulitis, major abscesses, or traumatic wound infections.

One trial was conducted primarily in the United States and South Africa (study 9801), and the second was conducted at non-US sites only (study 9901). The two trials were similar in design but differed in patient characteristics, including history of diabetes and peripheral vascular disease. There were a total of 534 adult patients treated with daptomycin and 558 treated with comparator in the two trials. The majority (89.7%) of patients received IV medication exclusively.

The efficacy endpoints in both trials were the clinical success rates in the intent-to-treat (ITT) population and in the clinically evaluable (CE) population. In study 9801, clinical success rates in the ITT population were 62.5% (165/264) in patients treated with daptomycin and 60.9% (162/266) in patients treated with comparator drugs. Clinical success rates in the CE population were 76.0% (158/208) in patients treated with daptomycin and 76.7% (158/206) in patients treated with comparator drugs. In study 9901, clinical success rates in the ITT population were 80.4% (217/270) in patients treated with daptomycin and 80.5% (235/292) in patients treated with comparator drugs. Clinical success rates in the CE population were 89.9% (214/238) in patients treated with daptomycin and 90.4% (226/250) in patients treated with comparator drugs.

The success rates by pathogen for microbiologically evaluable patients are presented in Table 16.

Table 16: Clinical Success Rates by Infecting Pathogen in the cSSSI Trials in Adult Patients (Population: Microbiologically Evaluable)
Pathogen | Success Rate n/N (%)
Pathogen | Daptomycin | Comparator*
Methicillin-susceptible Staphylococcus aureus (MSSA)† | 170/198 (86%) | 180/207 (87%)
Methicillin-resistant Staphylococcus aureus (MRSA)† | 21/28 (75%) | 25/36 (69%)
Streptococcus pyogenes | 79/84 (94%) | 80/88 (91%)
Streptococcus agalactiae | 23/27 (85%) | 22/29 (76%)
Streptococcus dysgalactiae subsp. equisimilis | 8/8 (100%) | 9/11 (82%)
Enterococcus faecalis (vancomycin-susceptible only) | 27/37 (73%) | 40/53 (76%)
*Comparator: vancomycin (1 g IV q12h) or an anti-staphylococcal semi-synthetic penicillin (i.e., nafcillin, oxacillin, cloxacillin, or flucloxacillin; 4 to 12 g/day IV in divided doses).
†As determined by the central laboratory.

Pediatric Patients (1 to 17 Years of Age) with cSSSI

The cSSSI pediatric trial was a single prospective multi-center, randomized, comparative trial. A total of 396 pediatric patients aged 1 to 17 years with cSSSI caused by Gram positive pathogens were enrolled into the study. Patients known to have bacteremia, osteomyelitis, endocarditis, and pneumonia at baseline were excluded. Patients were enrolled in a stepwise approach into four age groups and given age-dependent doses of daptomycin once daily for up to 14 days. The different age groups and doses evaluated were as follows: Adolescents (12 to 17 years) treated with 5 mg/kg of daptomycin (n=113), Children (7 to 11 years) treated with 7 mg/kg of daptomycin (n=113), Children (2 to 6 years) treated with 9 mg/kg of daptomycin (n=125) and Infants (1 to <2 years) treated with 10 mg/kg (n= 45).

Patients were randomized 2:1 to receive daptomycin or a standard of care (SOC) comparator, which included intravenous therapy with either vancomycin, clindamycin, or an anti-staphylococcal semi-synthetic penicillin (nafcillin, oxacillin, or cloxacillin). Patients could switch to oral therapy after clinical improvement was demonstrated (no minimum IV dosing was required).

The primary objective of this study was to evaluate the safety of daptomycin. The clinical outcome was determined by resolution or improvement of symptoms at the End-of-Treatment (EOT), 3 days after the last dose, and Test-of-Cure (TOC), 7 to 14 days after the last dose. Investigator observed outcomes were verified in a blinded fashion. Of the 396 subjects randomized in the study, 389 subjects were treated with daptomycin or comparator and included in the ITT population. Of these, 257 subjects were randomized to the daptomycin group and 132 subjects were randomized to the comparator group. Approximately 95% of subjects switched to oral therapy. The mean day of switch was day 4, and ranged from day 1 to day 14. The clinical success rates determined at 7 to 14 days after last dose of therapy (IV and oral) (TOC visit) were 88% (227/257) for daptomycin and 86% (114/132) for comparator.

14.2 S. aureus Bacteremia/Endocarditis

Adults with S. aureus Bacteremia/Endocarditis

The efficacy of daptomycin in the treatment of adult patients with S. aureus bacteremia was demonstrated in a randomized, controlled, multinational, multicenter, open-label trial. In this trial, adult patients with at least one positive blood culture for S. aureus obtained within 2 calendar days prior to the first dose of study drug and irrespective of source were enrolled and randomized to either daptomycin (6 mg/kg IV every 24h) or standard of care [an anti-staphylococcal semi-synthetic penicillin 2 g IV every 4h (nafcillin, oxacillin, cloxacillin, or flucloxacillin) or vancomycin 1 g IV every 12h, each with initial gentamicin 1 mg/kg IV every 8 hours for first 4 days]. Of the patients in the comparator group, 93% received initial gentamicin for a median of 4 days, compared with 1 patient (<1%) in the daptomycin group. Patients with prosthetic heart valves, intravascular foreign material that was not planned for removal within 4 days after the first dose of study medication, severe neutropenia, known osteomyelitis, polymicrobial bloodstream infections, creatinine clearance <30 mL/min, and pneumonia were excluded.

Upon entry, patients were classified for likelihood of endocarditis using the modified Duke criteria (Possible, Definite, or Not Endocarditis). Echocardiography, including a transesophageal echocardiogram (TEE), was performed within 5 days following study enrollment. The choice of comparator agent was based on the oxacillin susceptibility of the S. aureus isolate. The duration of study treatment was based on the investigator's clinical diagnosis. Final diagnoses and outcome assessments at Test of Cure (6 weeks after the last treatment dose) were made by a treatment-blinded Adjudication Committee, using protocol-specified clinical definitions and a composite primary efficacy endpoint (clinical and microbiological success) at the Test of Cure visit.

A total of 246 patients ≥18 years of age (124 daptomycin, 122 comparator) with S. aureus bacteremia were randomized from 48 centers in the US and Europe. In the ITT population, 120 patients received daptomycin and 115 received comparator (62 received an anti-staphylococcal semi-synthetic penicillin and 53 received vancomycin). Thirty-five patients treated with an anti-staphylococcal semi-synthetic penicillin received vancomycin initially for 1 to 3 days, pending final susceptibility results for the S. aureus isolates. The median age among the 235 patients in the ITT population was 53 years (range: 21 to 91 years); 30/120 (25%) in the daptomycin group and 37/115 (32%) in the comparator group were ≥65 years of age. Of the 235 ITT patients, there were 141 (60%) males and 156 (66%) Caucasians across the two treatment groups. In addition, 176 (75%) of the ITT population had systemic inflammatory response syndrome (SIRS) at baseline and 85 (36%) had surgical procedures within 30 days prior to onset of the S. aureus bacteremia. Eighty-nine patients (38%) had bacteremia caused by methicillin-resistant S. aureus (MRSA). Entry diagnosis was based on the modified Duke criteria and comprised 37 (16%) Definite, 144 (61%) Possible, and 54 (23%) Not Endocarditis. Of the 37 patients with an entry diagnosis of Definite Endocarditis, all (100%) had a final diagnosis of infective endocarditis, and of the 144 patients with an entry diagnosis of Possible Endocarditis, 15 (10%) had a final diagnosis of infective endocarditis as assessed by the Adjudication Committee. Of the 54 patients with an entry diagnosis of Not Endocarditis, 1 (2%) had a final diagnosis of infective endocarditis as assessed by the Adjudication Committee.

In the ITT population, there were 182 patients with bacteremia and 53 patients with infective endocarditis as assessed by the Adjudication Committee, including 35 with right-sided endocarditis and 18 with left-sided endocarditis. The 182 patients with bacteremia comprised 121 with complicated S. aureus bacteremia and 61 with uncomplicated S. aureus bacteremia.

Complicated bacteremia was defined as S. aureus isolated from blood cultures obtained on at least 2 different calendar days, and/or metastatic foci of infection (deep tissue involvement), and classification of the patient as not having endocarditis according to the modified Duke criteria. Uncomplicated bacteremia was defined as S. aureus isolated from blood culture(s) obtained on a single calendar day, no metastatic foci of infection, no infection of prosthetic material, and classification of the patient as not having endocarditis according to the modified Duke criteria. The definition of right-sided infective endocarditis (RIE) used in the clinical trial was Definite or Possible Endocarditis according to the modified Duke criteria and no echocardiographic evidence of predisposing pathology or active involvement of either the mitral or aortic valve. Complicated RIE comprised patients who were not intravenous drug users, had a positive blood culture for MRSA, serum creatinine ≥2.5 mg/dL, or evidence of extrapulmonary sites of infection. Patients who were intravenous drug users, had a positive blood culture for methicillin-susceptible S. aureus (MSSA), had serum creatinine <2.5 mg/dL, and were without evidence of extrapulmonary sites of infection were considered to have uncomplicated RIE.

The coprimary efficacy endpoints in the trial were the Adjudication Committee success rates at the Test of Cure visit (6 weeks after the last treatment dose) in the ITT and Per Protocol (PP) populations. The overall Adjudication Committee success rates in the ITT population were 44.2% (53/120) in patients treated with daptomycin and 41.7% (48/115) in patients treated with comparator (difference = 2.4% [95% CI −10.2, 15.1]). The success rates in the PP population were 54.4% (43/79) in patients treated with daptomycin and 53.3% (32/60) in patients treated with comparator (difference = 1.1% [95% CI −15.6, 17.8]).

Adjudication Committee success rates are shown in Table 17.

Table 17: Adjudication Committee Success Rates at Test of Cure in the S. aureus Bacteremia/Endocarditis Trial in Adult Patients (Population: ITT)
Population | Success Rate n/N (%) |  | Difference: Daptomycin − Comparator (Confidence Interval)
Population | Daptomycin 6 mg/kg | Comparator* | Difference: Daptomycin − Comparator (Confidence Interval)
Overall | 53/120 (44%) | 48/115 (42%) | 2.4% (−10.2, 15.1)†
Baseline Pathogen
Methicillin-susceptible S. aureus | 33/74 (45%) | 34/70 (49%) | −4.0% (−22.6, 14.6)‡
Methicillin-resistant S. aureus | 20/45 (44%) | 14/44 (32%) | 12.6% (−10.2, 35.5)‡
Entry Diagnosis§
Definite or Possible Infective Endocarditis | 41/90 (46%) | 37/91 (41%) | 4.9% (−11.6, 21.4)‡
Not Infective Endocarditis | 12/30 (40%) | 11/24 (46%) | −5.8% (−36.2, 24.5)‡
Final Diagnosis
Uncomplicated Bacteremia | 18/32 (56%) | 16/29 (55%) | 1.1% (−31.7, 33.9)¶
Complicated Bacteremia | 26/60 (43%) | 23/61 (38%) | 5.6% (−17.3, 28.6)¶
Right-Sided Infective Endocarditis | 8/19 (42%) | 7/16 (44%) | −1.6% (−44.9, 41.6)¶
Uncomplicated Right-Sided Infective Endocarditis | 3/6 (50%) | 1/4 (25%) | 25.0% (−51.6, 100.0)¶
Complicated Right-Sided Infective Endocarditis | 5/13 (39%) | 6/12 (50%) | −11.5% (−62.4, 39.4)¶
Left-Sided Infective Endocarditis | 1/9 (11%) | 2/9 (22%) | −11.1% (−55.9, 33.6)¶
*Comparator: vancomycin (1 g IV q12h) or an anti-staphylococcal semi-synthetic penicillin (i.e., nafcillin, oxacillin, cloxacillin, or flucloxacillin; 2 g IV q4h), each with initial low-dose gentamicin.
† 95% Confidence Interval
‡ 97.5% Confidence Interval (adjusted for multiplicity)
§ According to the modified Duke criteria^5
¶ 99% Confidence Interval (adjusted for multiplicity)

Eighteen (18/120) patients in the daptomycin arm and 19/116 patients in the comparator arm died during the trial. These comprise 3/28 daptomycin-treated patients and 8/26 comparator-treated patients with endocarditis, as well as 15/92 daptomycin-treated patients and 11/90 comparator-treated patients with bacteremia. Among patients with persisting or relapsing S. aureus infections, 8/19 daptomycin-treated patients and 7/11 comparator-treated patients died.

Overall, there was no difference in time to clearance of S. aureus bacteremia between daptomycin and comparator. The median time to clearance in patients with MSSA was 4 days and in patients with MRSA was 8 days.

Failure of treatment due to persisting or relapsing S. aureus infections was assessed by the Adjudication Committee in 19/120 (16%) daptomycin-treated patients (12 with MRSA and 7 with MSSA) and 11/115 (10%) comparator-treated patients (9 with MRSA treated with vancomycin and 2 with MSSA treated with an anti-staphylococcal semi-synthetic penicillin). Among all failures, isolates from 6 daptomycin-treated patients and 1 vancomycin-treated patient developed increasing MICs (reduced susceptibility) by central laboratory testing during or following therapy. Most patients who failed due to persisting or relapsing S. aureus infection had deep-seated infection and did not receive necessary surgical intervention [see Warnings and Precautions (5.9)].

Pediatric Patients (1 to 17 Years of Age) with S. aureus Bacteremia

The pediatric S. aureus bacteremia study was designed as a prospective multi-center, randomized, comparative trial to treat pediatric patients aged 1 to 17 years with bacteremia. Patients known to have endocarditis or pneumonia at baseline were excluded. Patients were enrolled in a stepwise approach into three age groups and given age-dependent doses of daptomycin once daily for up to 42 days. The different age groups and doses evaluated were as follows: Adolescents (12 to 17 years, n=14 patients) treated with daptomycin dosed at 7 mg/kg once daily, Children (7 to 11 years, n=19 patients) treated with daptomycin dosed at 9 mg/kg once daily and Children (2 to 6 years, n=22 patients) treated with daptomycin dosed at 12 mg/kg once daily. No patients 1 to <2 years of age were enrolled.

Patients were randomized 2:1 to receive daptomycin or a standard of care comparator, which included intravenous therapy with vancomycin, semi-synthetic penicillin, first generation cephalosporin or clindamycin. Patients could switch to oral therapy after clinical improvement was demonstrated (no minimum IV dosing was required).

The primary objective of this study was to assess the safety of daptomycin. The clinical outcome was determined by resolution or improvement of symptoms at test-of-cure (TOC) visit, 7 to 14 days after the last dose, which was assessed by the site level Blinded Evaluator.

Of the 82 subjects randomized in the study, 81 subjects were treated with daptomycin or comparator and included in the safety population, and 73 had a proven S. aureus bacteremia at Baseline. Of these, 51 subjects were randomized to the daptomycin group and 22 subjects were randomized to the comparator group. The mean duration of IV therapy was 12 days, with a range of 1 to 44 days. Forty-eight subjects switched to oral therapy, and the mean duration of oral therapy was 21 days. The clinical success rates determined at 7 to 14 days after last dose of therapy (IV and oral) (TOC visit) were 88% (45/51) for daptomycin and 77% (17/22) for comparator.

15 REFERENCES

1. Liu SL, Howard LC, Van Lier RBL, Markham JK: Teratology studies with daptomycin administered intravenously (iv) to rats and rabbits. Teratology 37(5):475, 1988.
2. Stroup JS, Wagner J, Badzinski T: Use of daptomycin in a pregnant patient with Staphylococcus aureus endocarditis. Ann Pharmacother 44(4):746-749, 2010.
3. Buitrago MI, Crompton JA, Bertolami S, North DS, Nathan RA. Extremely low excretion of daptomycin into breast milk of a nursing mother with methicillin-resistant Staphylococcus aureus pelvic inflammatory disease. Pharmacotherapy 2009;29(3):347–351.
4. Klibanov OM, Vickery S, Nortey C: Successful treatment of infective panniculitis with daptomycin in a pregnant, morbidly obese patient. Ann Pharmacother 48(5):652-655, 2014.
5. Li JS, Sexton DJ, Mick N, Nettles R, Fowler VG Jr, Ryan T, Bashore T, Corey GR. Proposed modifications to the Duke criteria for the diagnosis of infective endocarditis. Clin Infect Dis 2000; 30:633–638.

16 HOW SUPPLIED/STORAGE AND HANDLING

How Supplied

Daptomycin for Injection is supplied as a sterile, nonpyrogenic, preservative-free, pale yellow to light brown lyophilized cake in single-dose vials as follows:

NDC | Daptomycin for Injection | Package Factor
25021-179-15 | 350 mg Single-Dose Vial | 1 vial per carton
25021-179-16 | 350 mg Single-Dose Vial | 10 vials per carton

The container closure is not made with natural rubber latex.

Storage Conditions

Store refrigerated between 2°C and 8°C (36°F and 46° F); avoid excessive heat. Storage conditions for the reconstituted and diluted solutions are described in another section of the prescribing information [see Dosage and Administration (2.7)].

17 PATIENT COUNSELING INFORMATION

Allergic Reactions

Advise patients that allergic reactions, including serious skin, kidney, lung, or other organ reactions, could occur and that these serious reactions require immediate treatment. Patients should report any previous allergic reactions to daptomycin [see Warnings and Precautions (5.1, 5.4, 5.5)].

Muscle Pain or Weakness (Myopathy and Rhabdomyolysis, Peripheral Neuropathy)

Advise patients to report muscle pain or weakness, especially in the forearms and lower legs, as well as tingling or numbness [see Warnings and Precautions (5.2, 5.6)].

Cough, Breathlessness or Fever (Eosinophilic Pneumonia)

Advise patients to report any symptoms of cough, breathlessness, or fever [see Warnings and Precautions (5.3)].

C. difficile-Associated Diarrhea (CDAD)

Advise patients that diarrhea is a common problem caused by antibacterials that usually ends when the antibacterial is discontinued. Sometimes after starting treatment with antibacterials, including daptomycin, patients can develop watery and bloody stools (with or without stomach cramps and fever), even as late as 2 or more months after having received the last dose of the antibacterial. If this occurs, patients should contact their physician as soon as possible [see Warnings and Precautions (5.8)].

Antibacterial Resistance

Patients should be counseled that antibacterial drugs, including Daptomycin for Injection, should be used to treat bacterial infections. They do not treat viral infections (e.g., the common cold). When Daptomycin for Injection is prescribed to treat a bacterial infection, patients should be told that although it is common to feel better early in the course of therapy, the medication should be administered exactly as directed. Skipping doses or not completing the full course of therapy may (1) decrease the effectiveness of the immediate treatment and (2) increase the likelihood that bacteria will develop resistance and will not be treatable by Daptomycin for Injection or other antibacterial drugs in the future.

Brands listed are the trademarks of their respective owners.

SAGENT®
Mfd. for SAGENT Pharmaceuticals
Schaumburg, IL 60195 (USA)
Made in India
©2023 Sagent Pharmaceuticals

SAGENT Pharmaceuticals ®

PACKAGE LABEL – PRINCIPAL DISPLAY PANEL – Vial Label

NDC 25021-179-15

Rx only

DAPTOMYCIN FOR INJECTION

350 mg per vial

Must Be Refrigerated

Must Be Reconstituted

For Intravenous Use Only

Single-Dose Vial